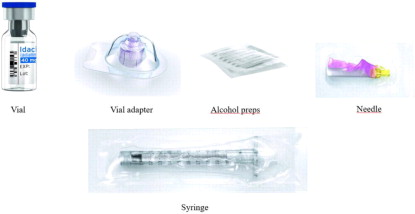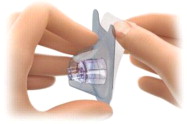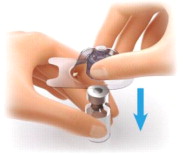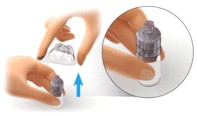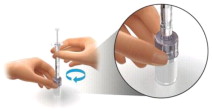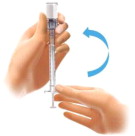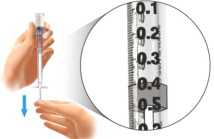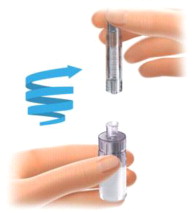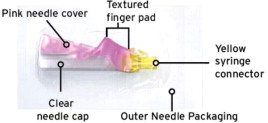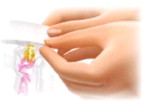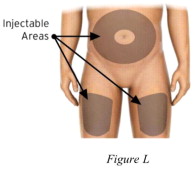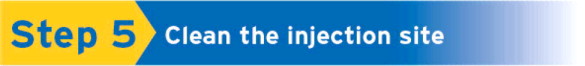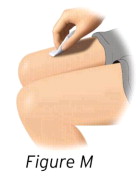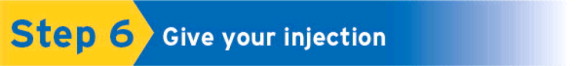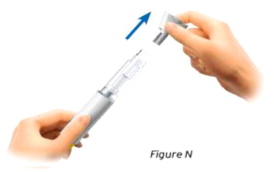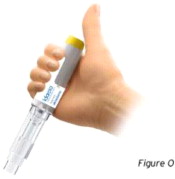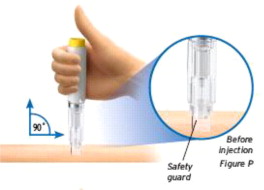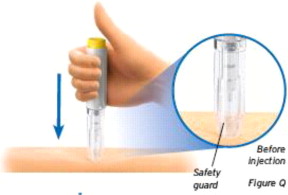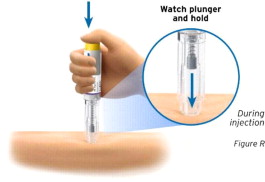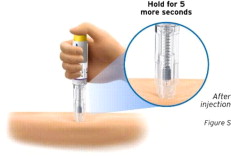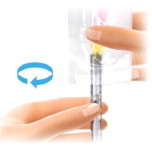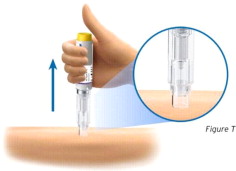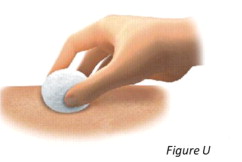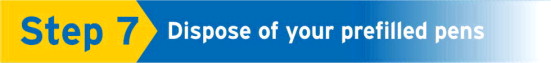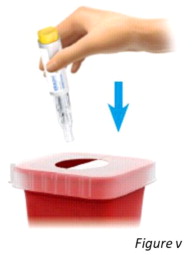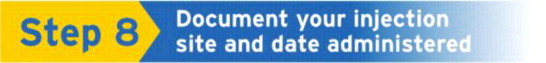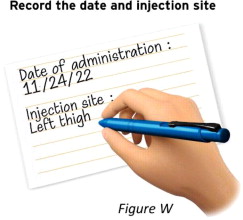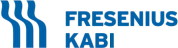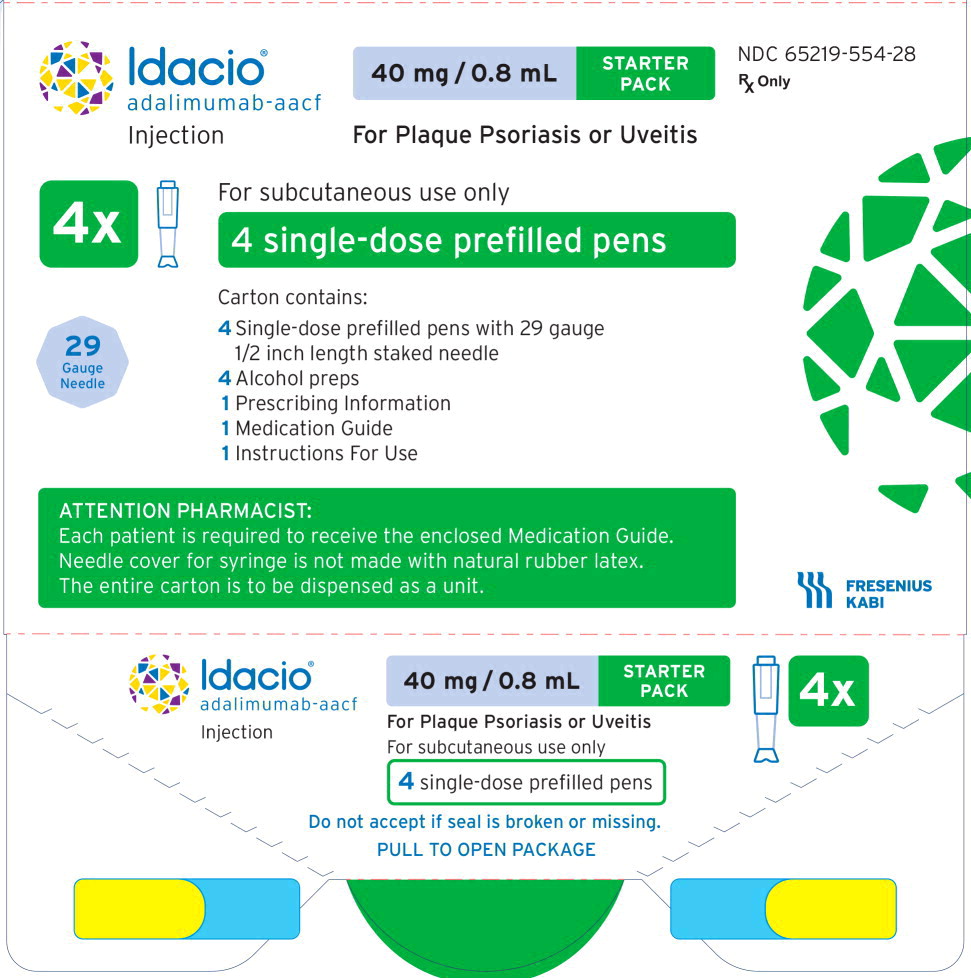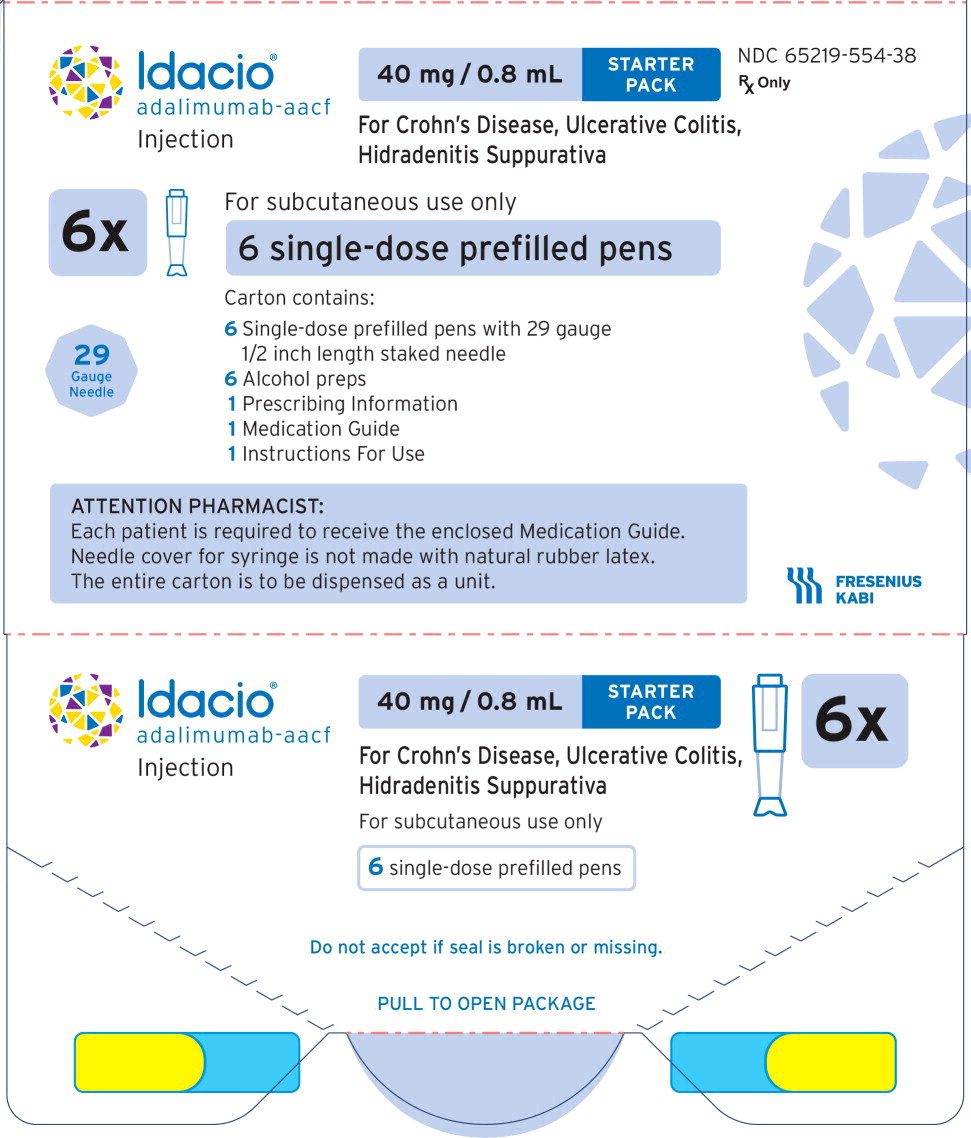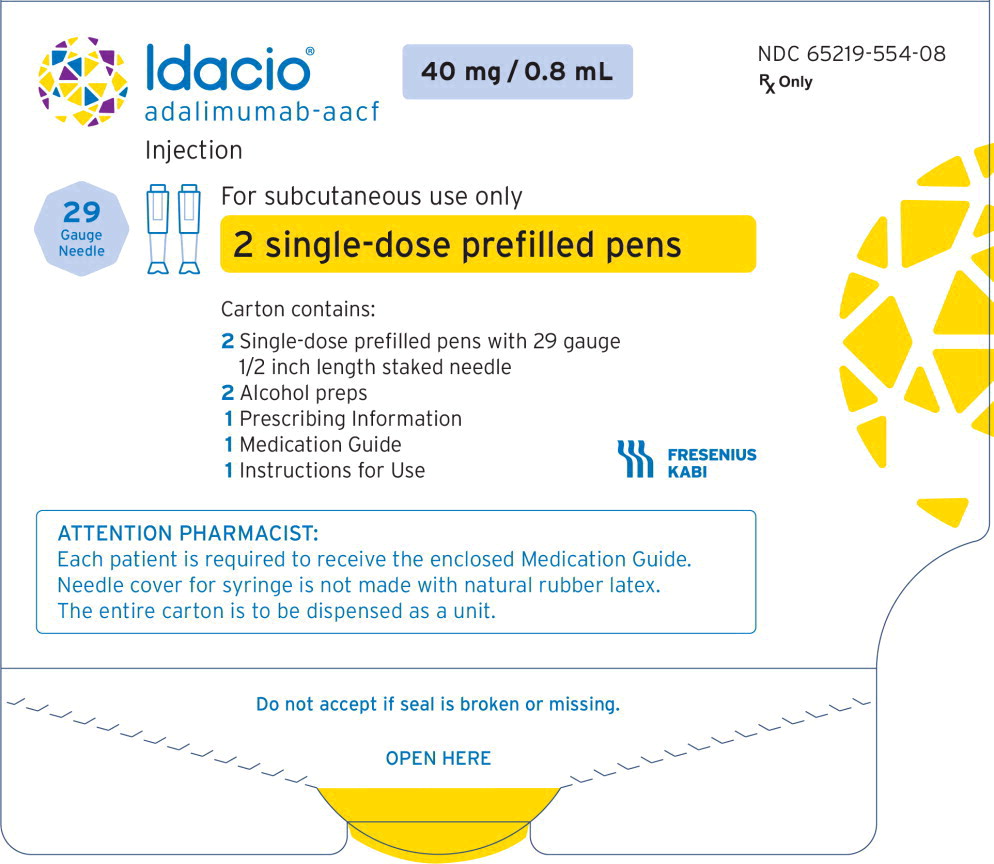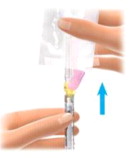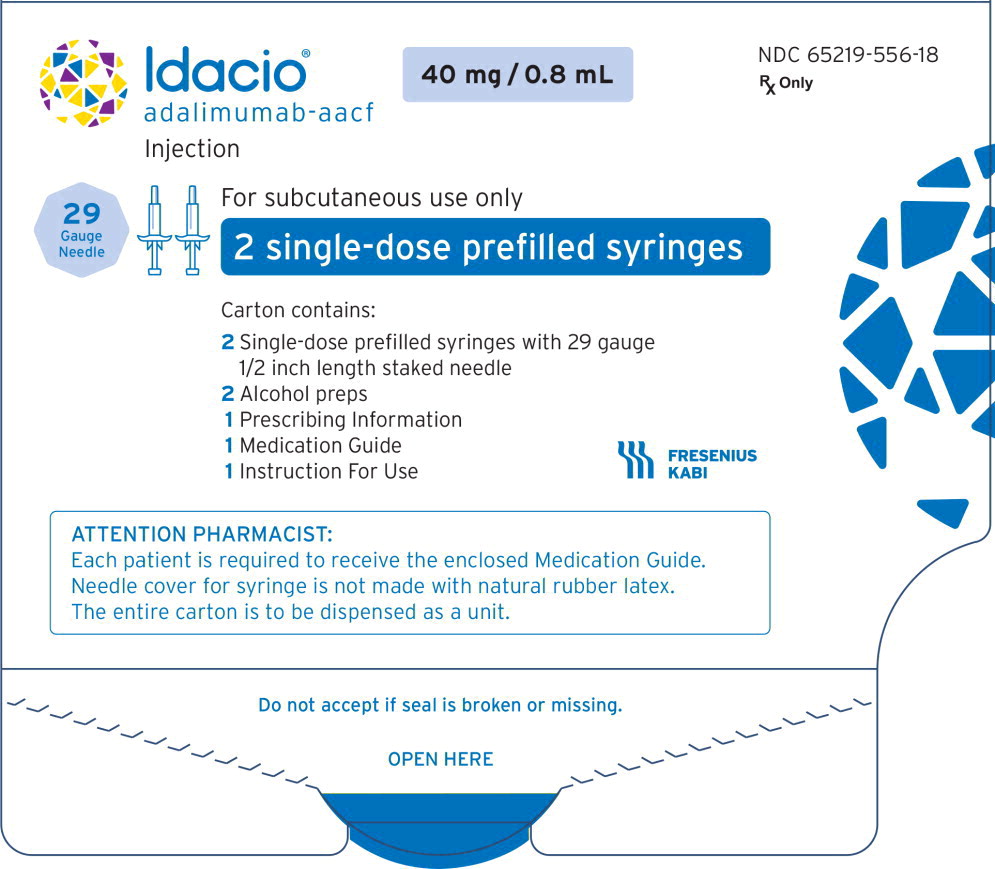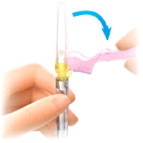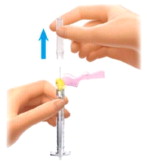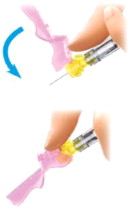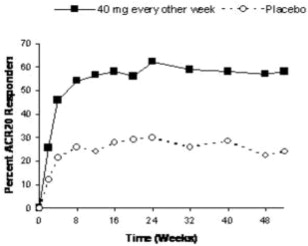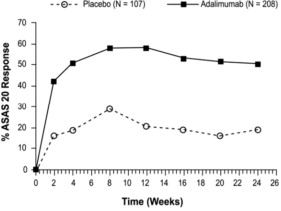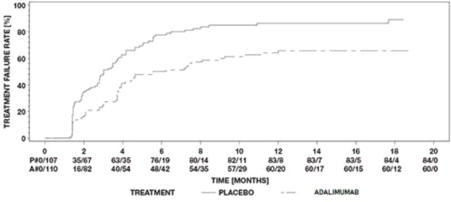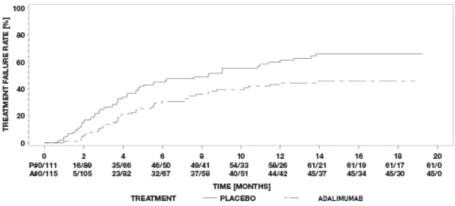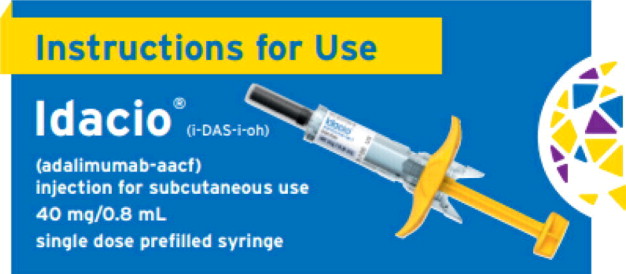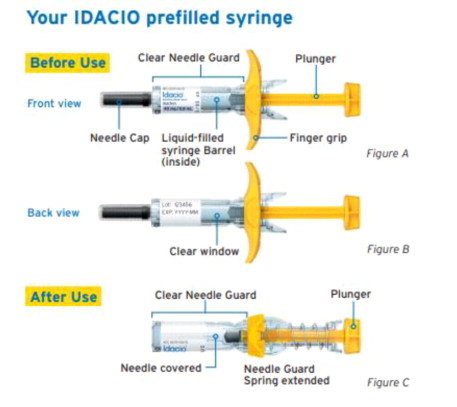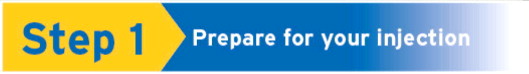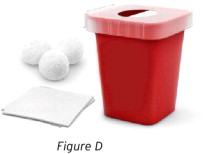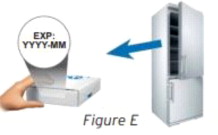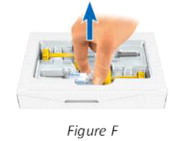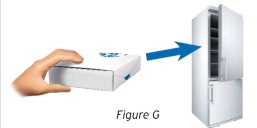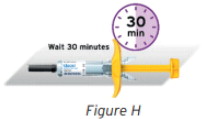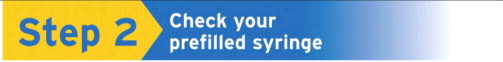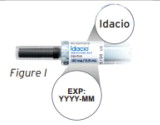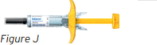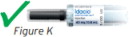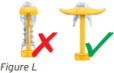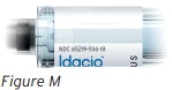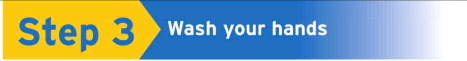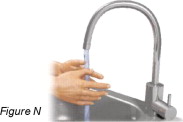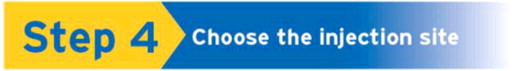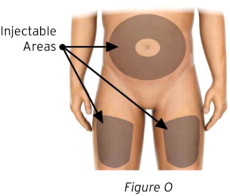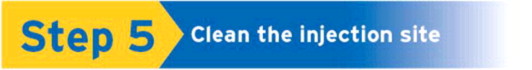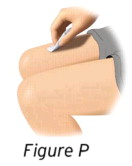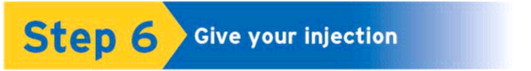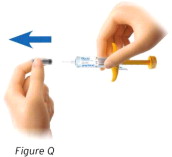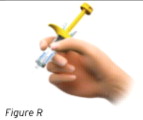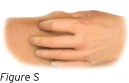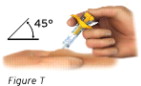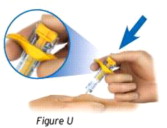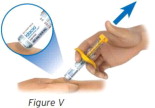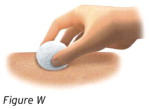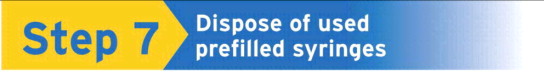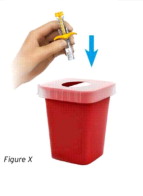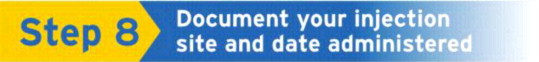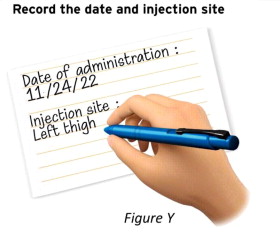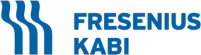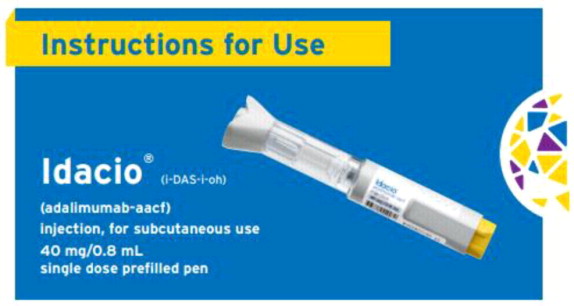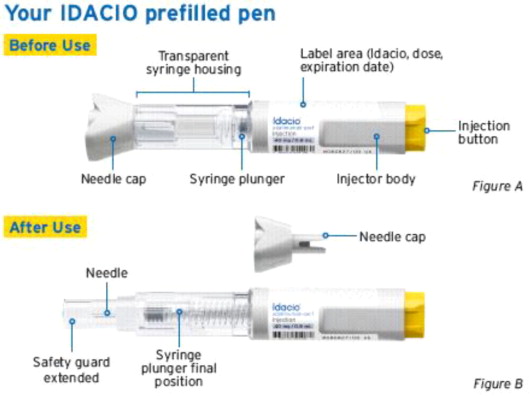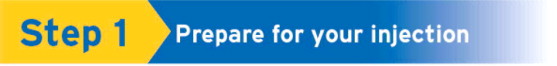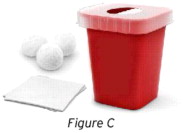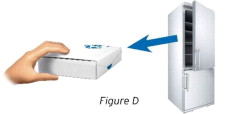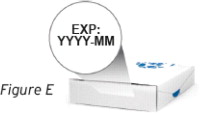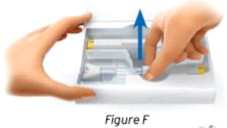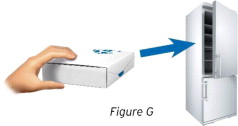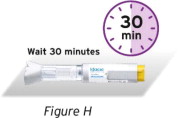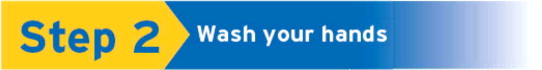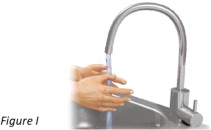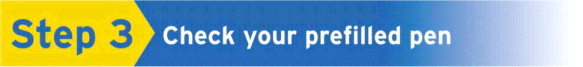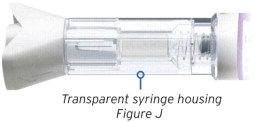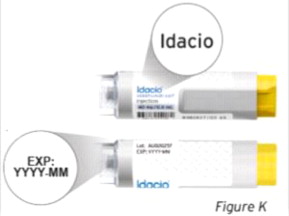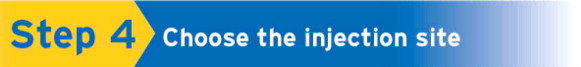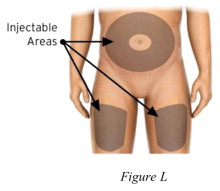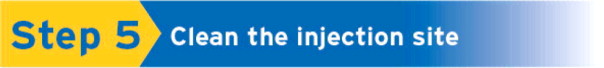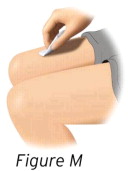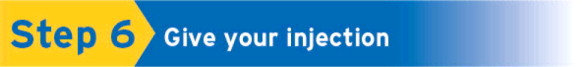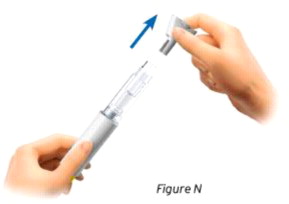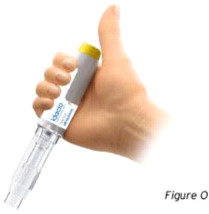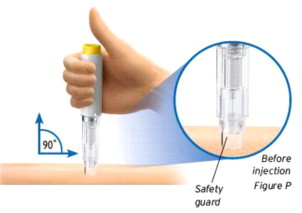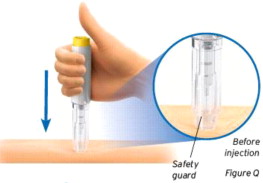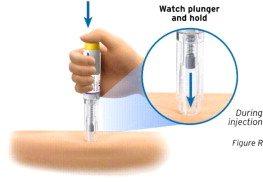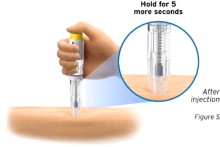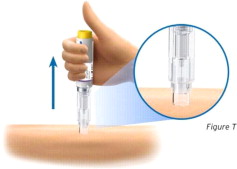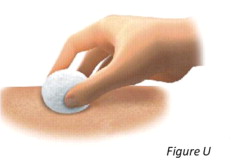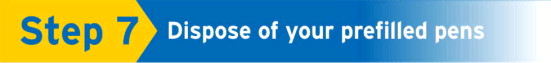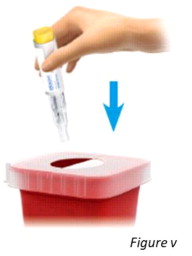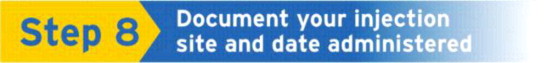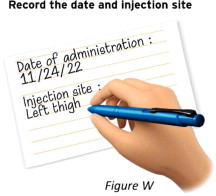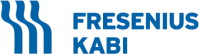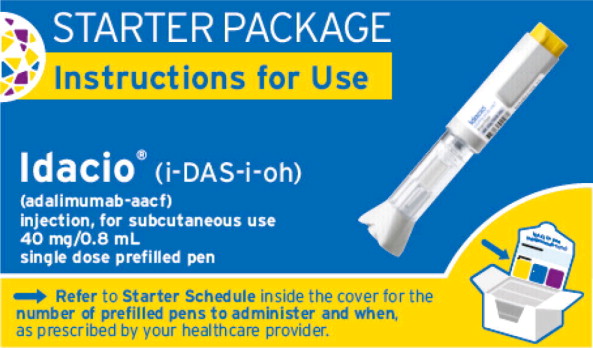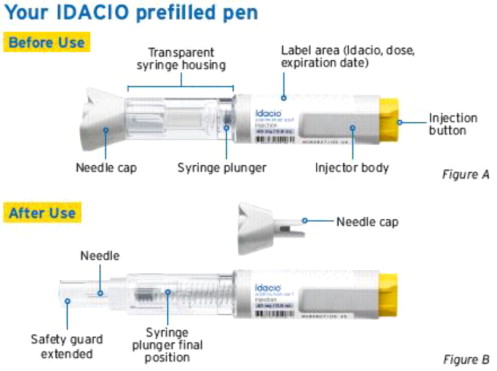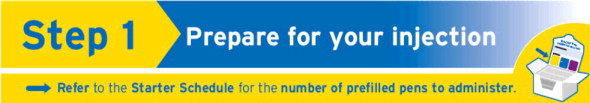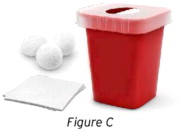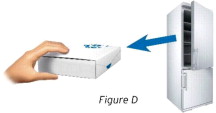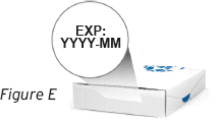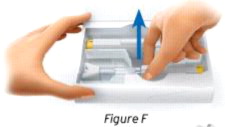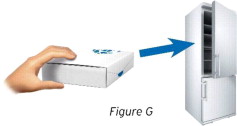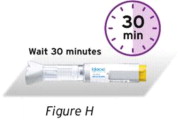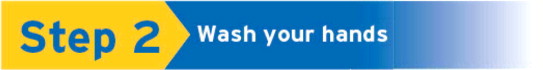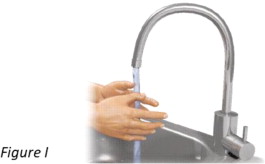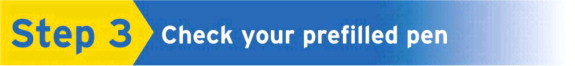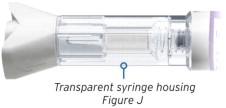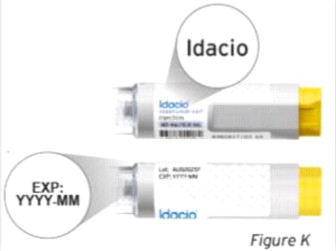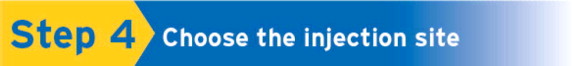 DRUG LABEL: Idacio
NDC: 65219-556 | Form: KIT | Route: SUBCUTANEOUS
Manufacturer: Fresenius Kabi USA, LLC
Category: prescription | Type: HUMAN PRESCRIPTION DRUG LABEL
Date: 20260130

ACTIVE INGREDIENTS: adalimumab 40 mg/0.8 mL; Isopropyl alcohol 0.75 g/1 1
INACTIVE INGREDIENTS: acetic acid; trehalose dihydrate; polysorbate 80; sodium chloride; water; Sodium hydroxide; Water

HIGHLIGHTS OF PRESCRIBING INFORMATION

These highlights do not include all the information needed to use IDACIO safely and effectively. See full prescribing information for IDACIO.
IDACIO® (adalimumab-aacf) injection, for subcutaneous use
Initial U.S. Approval: 2022
IDACIO® (adalimumab-aacf) is biosimilar [Biosimilar means that the biological product is approved based on data demonstrating that it is highly similar to an FDA-approved biological product, known as a reference product, and that there are no clinically meaningful differences between the biosimilar product and the reference product. Biosimilarity of IDACIO has been demonstrated for the condition(s) of use (e.g. indication(s), dosing regimen(s)), strength(s), dosage form(s), and route(s) of administration described in its Full Prescribing Information.] to HUMIRA® (adalimumab).

RECENT MAJOR CHANGES

Indications and Usage, Hidradenitis Suppurativa (1.8) | 10/2023
Indications and Usage, Uveitis (1.9) | 10/2023
Dosage and Administration, Juvenile Idiopathic Arthritis (2.2) | 1/2024
Dosage and Administration, Crohn's Disease (2.3) | 1/2024
Dosage and Administration, Plaque Psoriasis or Adult Uveitis (2.5) | 10/2023
Dosage and Administration, Hidradenitis Suppurativa (2.6) | 10/2023
Dosage and Administration, General Considerations For Administration (2.8) | 1/2024
Warnings and Precautions, Malignancies (5.2) | 10/2023
Warnings and Precautions, Neurological Reactions (5.5) | 10/2023

WARNING: SERIOUS INFECTIONS and MALIGNANCY

See full prescribing information for complete boxed warning.

SERIOUS INFECTIONS (5.1, 6.1):

- Increased risk of serious infections leading to hospitalization or death, including tuberculosis (TB), bacterial sepsis, invasive fungal infections (such as histoplasmosis), and infections due to other opportunistic pathogens.
- Discontinue IDACIO if a patient develops a serious infection or sepsis during treatment.
- Perform test for latent TB; if positive, start treatment for TB prior to starting IDACIO.
- Monitor all patients for active TB during treatment, even if initial latent TB test is negative.

MALIGNANCY (5.2) :

- Lymphoma and other malignancies, some fatal, have been reported in children and adolescent patients treated with TNF blockers including adalimumab products.
- Post-marketing cases of hepatosplenic T-cell lymphoma (HSTCL), a rare type of T-cell lymphoma, have occurred in adolescent and young adults with inflammatory bowel disease treated with TNF blockers including adalimumab products.

1 INDICATIONS AND USAGE

IDACIO is a tumor necrosis factor (TNF) blocker indicated for:

- Rheumatoid Arthritis (RA) (1.1): reducing signs and symptoms, inducing major clinical response, inhibiting the progression of structural damage, and improving physical function in adult patients with moderately to severely active RA.
- Juvenile Idiopathic Arthritis (JIA) (1.2): reducing signs and symptoms of moderately to severely active polyarticular JIA in patients 2 years of age and older.
- Psoriatic Arthritis (PsA) (1.3): reducing signs and symptoms, inhibiting the progression of structural damage, and improving physical function in adult patients with active PsA.
- Ankylosing Spondylitis (AS) (1.4): reducing signs and symptoms in adult patients with active AS.
- Crohn's Disease (CD) (1.5): treatment of moderately to severely active Crohn's disease in adults and pediatric patients 6 years of age and older.
- Ulcerative Colitis (UC) (1.6): treatment of moderately to severely active ulcerative colitis in adult patients.
- Limitations of Use: Effectiveness has not been established in patients who have lost response to or were intolerant to TNF blockers.
- Plaque Psoriasis (Ps) (1.7): treatment of adult patients with moderate to severe chronic plaque psoriasis who are candidates for systemic therapy or phototherapy, and when other systemic therapies are medically less appropriate.
- Hidradenitis Suppurativa (HS) (1.8): treatment of moderate to severe hidradenitis suppurativa in adult patients.
- Uveitis (UV) (1.9): treatment of non-infectious intermediate, posterior, and panuveitis in adult patients.

2 DOSAGE AND ADMINISTRATION

- Administer by subcutaneous injection (2)

Rheumatoid Arthritis, Psoriatic Arthritis, Ankylosing Spondylitis (2.1):

- Adults: 40 mg every other week.
  - Some patients with RA not receiving methotrexate may benefit from increasing the dosage to 40 mg every week or 80 mg every other week.

Juvenile Idiopathic Arthritis (2.2):

Pediatric Weight 2 Years of Age and Older | Recommended Dosage
10 kg (22 lbs) to less than 15 kg (33 lbs) | 10 mg every other week
15 kg (33 lbs) to less than 30 kg (66 lbs) | 20 mg every other week
30 kg (66 lbs) and greater | 40 mg every other week

Crohn's Disease (2.3):

- Adults: 160 mg on Day 1 (given in one day or split over two consecutive days); 80 mg on Day 15; and 40 mg every other week starting on Day 29.
- Pediatric Patients 6 Years of Age and Older:

Pediatric Weight | Recommended Dosage
 | Days 1 and 15 | Starting on Day 29
17 kg (37 lbs) to less than 40 kg (88 lbs) | Day 1: 80 mg Day 15: 40 mg | 20 mg every other week
40 kg (88 lbs) and greater | Day 1: 160 mg (single dose or split over two consecutive days) Day 15: 80 mg | 40 mg every other week

Ulcerative Colitis (2.4):

- Adults: 160 mg on Day 1 (given in one day or split over two consecutive days), 80 mg on Day 15 and 40 mg every other week starting on Day 29. Discontinue in patients without evidence of clinical remission by eight weeks (Day 57).

Plaque Psoriasis or Adult Uveitis (2.5):

- Adults: 80 mg initial dose, followed by 40 mg every other week starting one week after initial dose.

Hidradenitis Suppurativa (2.6):

- Adults:
  - Day 1: 160 mg (given in one day or split over two consecutive days)
  - Day 15: 80 mg
  - Day 29 and subsequent doses: 40 mg every week or 80 mg every other week

3 DOSAGE FORMS AND STRENGTHS

Injection:

- Single-dose prefilled pen (IDACIO Pen): 40 mg/0.8 mL (3)
- Single-dose prefilled glass syringe: 40 mg/0.8 mL (3)
- Single dose glass vial kit for institutional use only: 40mg/0.8 mL (3)

4 CONTRAINDICATIONS

None (4)

5 WARNINGS AND PRECAUTIONS

- Serious infections: Do not start IDACIO during an active infection. If an infection develops, monitor carefully, and stop IDACIO if infection becomes serious. (5.1)
- Invasive fungal infections: For patients who develop a systemic illness on IDACIO, consider empiric antifungal therapy for those who reside or travel to regions where mycoses are endemic. (5.1)
- Malignancies: Incidence of malignancies was greater in adalimumab-treated patients than in controls (5.2)
- Anaphylaxis or serious hypersensitivity reactions may occur (5.3)
- Hepatitis B virus reactivation: Monitor HBV carriers during and several months after therapy. If reactivation occurs, stop IDACIO and begin anti- viral therapy. (5.4)
- Demyelinating disease: Exacerbation or new onset, may occur. (5.5)
- Cytopenias, pancytopenia: Advise patients to seek immediate medical attention if symptoms develop and consider stopping IDACIO. (5.6)
- Heart failure: Worsening or new onset, may occur. (5.8)
- Lupus-like syndrome: Stop IDACIO if syndrome develops. (5.9)

6 ADVERSE REACTIONS

Most common adverse reactions (>10%) are infections (e.g. upper respiratory, sinusitis), injection site reactions, headache and rash. (6.1)

To report SUSPECTED ADVERSE REACTIONS, contact Fresenius Kabi USA, LLC at 1-800-551-7176 or FDA at 1-800-FDA-1088- or www.fda.gov/medwatch

7 DRUG INTERACTIONS

- Abatacept: Increased risk of serious infection. (5.1, 5.11, 7.2)
- Anakinra: Increased risk of serious infection. (5.1, 5.7, 7.2)
- Live vaccines: Avoid use with IDACIO. (5.10, 7.3)

FULL PRESCRIBING INFORMATION

WARNING: SERIOUS INFECTIONS and MALIGNANCY

SERIOUS INFECTIONS

Patients treated with adalimumab products including IDACIO are at increased risk for developing serious infections that may lead to hospitalization or death [see Warnings and Precautions (5.1)]. Most patients who developed these infections were taking concomitant immunosuppressants such as methotrexate or corticosteroids.

Discontinue IDACIO if a patient develops a serious infection or sepsis. Reported infections include:

- Active tuberculosis (TB), including reactivation of latent TB. Patients with TB have frequently presented with disseminated or extrapulmonary disease. Test patients for latent TB before IDACIO use and during therapy. Initiate treatment for latent TB prior to IDACIO use.
- Invasive fungal infections, including histoplasmosis, coccidioidomycosis, candidiasis, aspergillosis, blastomycosis, and pneumocystosis. Patients with histoplasmosis or other invasive fungal infections may present with disseminated, rather than localized, disease. Antigen and antibody testing for histoplasmosis may be negative in some patients with active infection. Consider empiric anti- fungal therapy in patients at risk for invasive fungal infections who develop severe systemic illness.
- Bacterial, viral and other infections due to opportunistic pathogens, including Legionella and Listeria.

Carefully consider the risks and benefits of treatment with IDACIO prior to initiating therapy in patients with chronic or recurrent infection.

Monitor patients closely for the development of signs and symptoms of infection during and after treatment with IDACIO, including the possible development of TB in patients who tested negative for latent TB infection prior to initiating therapy [see Warnings and Precautions (5.1) and Adverse Reactions (6.1)].

MALIGNANCY

Lymphoma and other malignancies, some fatal, have been reported in children and adolescent patients treated with TNF blockers including adalimumab products [see Warnings and Precautions (5.2)]. Post-marketing cases of hepatosplenic T-cell lymphoma (HSTCL), a rare type of T-cell lymphoma, have been reported in patients treated with TNF blockers including adalimumab products. These cases have had a very aggressive disease course and have been fatal. The majority of reported TNF blocker cases have occurred in patients with Crohn's disease or ulcerative colitis and the majority were in adolescent and young adult males. Almost all these patients had received treatment with azathioprine or 6-mercaptopurine (6–MP) concomitantly with a TNF blocker at or prior to diagnosis. It is uncertain whether the occurrence of HSTCL is related to use of a TNF blocker or a TNF blocker in combination with these other immunosuppressants [see Warnings and Precautions (5.2)].

1 INDICATIONS AND USAGE

1.1 Rheumatoid Arthritis

IDACIO is indicated for reducing signs and symptoms, inducing major clinical response, inhibiting the progression of structural damage, and improving physical function in adult patients with moderately to severely active rheumatoid arthritis. IDACIO can be used alone or in combination with methotrexate or other non-biologic disease-modifying anti-rheumatic drugs (DMARDs).

1.2 Juvenile Idiopathic Arthritis

IDACIO is indicated for reducing signs and symptoms of moderately to severely active polyarticular juvenile idiopathic arthritis in patients 2 years of age and older. IDACIO can be used alone or in combination with methotrexate.

1.3 Psoriatic Arthritis

IDACIO is indicated for reducing signs and symptoms, inhibiting the progression of structural damage, and improving physical function in adult patients with active psoriatic arthritis.

IDACIO can be used alone or in combination with non-biologic DMARDs.

1.4 Ankylosing Spondylitis

IDACIO is indicated for reducing signs and symptoms in adult patients with active ankylosing spondylitis.

1.5 Crohn's Disease

IDACIO is indicated for the treatment of moderately to severely active Crohn's disease in adults and pediatric patients 6 years of age and older.

1.6 Ulcerative Colitis

IDACIO is indicated for the treatment of moderately to severely active ulcerative colitis in adult patients.

Limitations of Use

The effectiveness of adalimumab products has not been established in patients who have lost response to or were intolerant to TNF blockers [see Clinical Studies (14.7)].

1.7 Plaque Psoriasis

IDACIO is indicated for the treatment of adult patients with moderate to severe chronic plaque psoriasis who are candidates for systemic therapy or phototherapy, and when other systemic therapies are medically less appropriate. IDACIO should only be administered to patients who will be closely monitored and have regular follow-up visits with a physician [see Warnings and Precautions (5)].

1.8 Hidradenitis Suppurativa

IDACIO is indicated for the treatment of moderate to severe hidradenitis suppurativa in adult patients.

1.9 Uveitis

IDACIO is indicated for the treatment of non-infectious intermediate, posterior, and panuveitis in adult patients.

2 DOSAGE AND ADMINISTRATION

2.1 Rheumatoid Arthritis, Psoriatic Arthritis, and Ankylosing Spondylitis

The recommended subcutaneous dosage of IDACIO for adult patients with rheumatoid arthritis (RA), psoriatic arthritis (PsA), or ankylosing spondylitis (AS) is 40 mg administered every other week. Methotrexate (MTX), other non-biologic DMARDS, glucocorticoids, nonsteroidal anti- inflammatory drugs (NSAIDs), and/or analgesics may be continued during treatment with IDACIO. In the treatment of RA, some patients not taking concomitant MTX may derive additional benefit from increasing the dosage of IDACIO to 40 mg every week or 80 mg every other week.

2.2 Juvenile Idiopathic Arthritis

The recommended subcutaneous dosage of IDACIO for patients 2 years of age and older with polyarticular juvenile idiopathic arthritis (JIA) is based on weight as shown below. MTX, glucocorticoids, NSAIDs, and/or analgesics may be continued during treatment with IDACIO.

Pediatric Weight (2 Years of Age and older) | Recommended Dosage
10 kg (22 lbs) to less than 15 kg (33 lbs) | 10 mg every other week
15 kg (33 lbs) to less than 30 kg (66 lbs) | 20 mg every other week
30 kg (66 lbs) and greater | 40 mg every other week

The only dosage form for IDACIO that allows weight-based dosing for pediatric patients below 30 kg is the single-dose glass vial kit for institutional use only.

Adalimumab products have not been studied in patients with polyarticular JIA less than 2 years of age or in patients with a weight below 10 kg.

2.3 Crohn's Disease

Adults

The recommended subcutaneous dosage of IDACIO for adult patients with Crohn's disease (CD) is 160 mg initially on Day 1 (given in one day or split over two consecutive days), followed by 80 mg two weeks later (Day 15). Two weeks later (Day 29) begin a dosage of 40 mg every other week. Aminosalicylates and/or corticosteroids may be continued during treatment with IDACIO. Azathioprine, 6-mercaptopurine (6-MP) [see Warnings and Precautions (5.2)] or MTX may be continued during treatment with IDACIO if necessary.

Pediatrics

The recommended subcutaneous dosage of IDACIO for pediatric patients 6 years of age and older with Crohn's disease (CD) is based on body weight as shown below:

Pediatric Weight | Recommended Dosage
Pediatric Weight | Days 1 through 15 | Starting on Day 29
17 kg (37 lbs) to less than 40 kg (88 lbs) | Day 1: 80 mg Day 15: 40 mg | 20 mg every other week
40 kg (88 lbs) and greater | Day 1: 160 mg (single dose or split over two consecutive days) Day 15: 80 mg | 40 mg every other week

The only dosage form for IDACIO that allows weight-based dosing for pediatric patients below 40 kg is the single-dose glass vial kit for institutional use only

2.4 Ulcerative Colitis

Adults

The recommended subcutaneous dosage of IDACIO for adult patients with ulcerative colitis is 160 mg initially on Day 1 (given in one day or split over two consecutive days), followed by 80 mg two weeks later (Day 15). Two weeks later (Day 29) continue with a dosage of 40 mg every other week.

Discontinue IDACIO in adult patients without evidence of clinical remission by eight weeks (Day 57) of therapy. Aminosalicylates and/or corticosteroids may be continued during treatment with IDACIO. Azathioprine and 6-mercaptopurine (6-MP) [see Warnings and Precautions (5.2)] may be continued during treatment with IDACIO if necessary.

2.5 Plaque Psoriasis or Adult Uveitis

The recommended subcutaneous dosage of IDACIO for adult patients with plaque psoriasis (Ps) or Uveitis (UV) is an initial dose of 80 mg, followed by 40 mg given every other week starting one week after the initial dose. The use of adalimumab products in moderate to severe chronic Ps beyond one year has not been evaluated in controlled clinical studies.

2.6 Hidradenitis Suppurativa

Adults

The recommended subcutaneous dosage of IDACIO for adult patients with hidradenitis suppurativa (HS) is an initial dose of 160 mg (given in one day or split over two consecutive days), followed by 80 mg two weeks later (Day 15). Begin 40 mg weekly or 80 mg every other week dosing two weeks later (Day 29).

2.7 Monitoring to Assess Safety

Prior to initiating IDACIO and periodically during therapy, evaluate patients for active tuberculosis and test for latent infection [see Warnings and Precautions (5.1)].

2.8 General Considerations for Administration

IDACIO Pen or prefilled syringe is intended for use under the guidance and supervision of a physician. A patient may self-inject IDACIO or a caregiver may inject IDACIO using either the IDACIO Pen or prefilled syringe if a physician determines that it is appropriate, and with medical follow-up, as necessary, after proper training in subcutaneous injection technique.

IDACIO may be taken out of the refrigerator for 15 to 30 minutes before injecting to allow the liquid to come to room temperature. Do not remove the cap or cover while allowing it to reach room temperature. Carefully inspect the solution in the IDACIO Pen, or prefilled syringe or single dose institutional use vial for particulate matter and discoloration prior to subcutaneous administration. If particulates and discolorations are noted, do not use the product. IDACIO does not contain preservatives. Therefore, discard unused portions of drug remaining in the syringe.

Instruct patients using the IDACIO Pen or prefilled syringe to inject the full amount in the syringe, according to the directions provided in the Instructions for Use [see Instructions for Use].

Injections should occur at separate sites in the thigh or abdomen. Rotate injection sites and do not give injections into areas where the skin is tender, bruised, red or hard.

If a dose is missed, administer the dose as soon as possible. Thereafter, resume dosing at the regular scheduled time.

The IDACIO syringe plunger stopper and needle cover are not made with natural rubber latex.

The IDACIO single-dose institutional use vial kit is for administration within an institutional setting only, such as a hospital, physician's office, or clinic. Withdraw the dose using the vial adapter, the sterile syringe and needle provided. Only administer one dose per vial. The vial does not contain preservatives; discard unused portion.

The IDACIO vial and syringe stopper are not made with natural rubber latex.

Read these Administration Instructions before using the Idacio Vial kit.

IDACIO is supplied in a carton containing 1 sterile single-use syringe, 1 sterile needle, 1 vial adapter, 2 alcohol preps and 1 glass vial providing 40 mg/0.8 mL of IDACIO (Figure A)

The contents of the Idacio Vial Kit are for single-dose (one-time) use only. Discard unused portion.

Figure A

Prior to Administration

- Remove the Idacio Vial Kit from the refrigerator and let it sit at room temperature for at least 30 minutes.
- Check the expiration date.
- Remove Vial Kit contents from the carton and inspect for damage.

Do not use if any kit component or packaging has been damaged.

- Check the vial contents to make sure that the liquid is clear, colorless, and free of particles and flakes.

Note: Prepare syringe just prior to administration and inject immediately. Do not store Idacio in the syringe.

Step 1. Prepare Vial and Vial Adapter

1.1 Remove plastic flip off cap from vial and disinfect the rubber stopper.
Do not touch the top of the vial after cleaning.

1.2 Without removing the vial adapter from its packaging, peel off the top cover (Figure B).
Do not touch the vial adapter.

Figure B

1.3 With the vial adapter still in its packaging, push the vial adapter onto the vial top until it snaps in place (Figure C).

Figure C

1.4 Remove the vial adapter packaging (Figure D)

Figure D

Step 2. Connect Syringe to Vial Adapter

2.1 Remove syringe from outer packaging.
Do not touch the syringe tip.

2.2 Hold the base of the vial adapter and connect the syringe to the vial adapter by turning it clockwise (Figure E).

Figure E

Step 3. Withdraw the Dose

3.1 Invert the vial completely with the vial adapter and syringe still connected (Figure F).

Figure F

3.2 Slowly withdraw the prescribed dose of Idacio into the syringe for administration (Figure G). Remove air bubbles from the syringe.
Do not pull the plunger rod out.

Figure G

Step 4. Disconnect the syringe

4.1 Turn over the vial and syringe. Hold the base of the vial adapter and disconnect the syringe from the vial adapter by turning it counterclockwise (Figure H).
Do not touch the syringe tip.

Figure H

Step 5. Attach Needle

Figure I

5.1 Peel open the outer needle packaging to uncover the yellow syringe connector (Figure J).

Figure J

5.2 Insert the syringe tip into the syringe connector. Turn the syringe connector in a clockwise direction to tighten (Figure K).

Figure K

5.3 Pull the outer needle packaging off (Figure L).
Do not remove the clear needle cap.

Figure L

5.4 Pull back the needle safety cover toward the syringe (Figure M).
Do not remove the needle cover from the connector.

Figure M

Step 6. Administer medication

6.1 When you are ready to inject Idacio remove the clear needle cap by pulling it straight off and throw it away (Figure N).
Do not recap the needle.

Figure N

6.2 Administer the dose subcutaneously.

6.3 Place your thumb or index finger on the center of the textured finger pad and push the pink needle safety cover forward over the needle until you hear it click or feel it lock (Figure O).

Figure O

Step 7. Discard Used Syringe and Needle

7.1 Discard used syringe and needle into an appropriate sharps container.

3 DOSAGE FORMS AND STRENGTHS

IDACIO is a clear and colorless to pale yellow solution available as:

- Pen (IDACIO Pen)
  Injection: 40 mg/0.8 mL in a single-dose pen.
- Prefilled Syringe
  Injection: 40 mg/0.8 mL in a single-dose prefilled glass syringe.
- Single-Dose Institutional Use Vial Kit
  Injection: 40 mg/0.8 mL in a single-dose, glass vial kit for institutional use only.

4 CONTRAINDICATIONS

None.

5 WARNINGS AND PRECAUTIONS

5.1 Serious Infections

Patients treated with adalimumab products including IDACIO are at increased risk for developing serious infections involving various organ systems and sites that may lead to hospitalization or death. Opportunistic infections due to bacterial, mycobacterial, invasive fungal, viral, parasitic, or other opportunistic pathogens including aspergillosis, blastomycosis, candidiasis, coccidioidomycosis, histoplasmosis, legionellosis, listeriosis, pneumocystosis and tuberculosis have been reported with TNF blockers. Patients have frequently presented with disseminated rather than localized disease.

The concomitant use of a TNF blocker and abatacept or anakinra was associated with a higher risk of serious infections in patients with rheumatoid arthritis (RA); therefore, the concomitant use of IDACIO and these biologic products is not recommended in the treatment of patients with RA [see Warnings and Precautions (5.7, 5.11) and Drug Interactions (7.2)].

Treatment with IDACIO should not be initiated in patients with an active infection, including localized infections. Patients 65 years of age and older, patients with co-morbid conditions and/or patients taking concomitant immunosuppressants (such as corticosteroids or methotrexate), may be at greater risk of infection. Consider the risks and benefits of treatment prior to initiating therapy in patients:

- with chronic or recurrent infection;
- who have been exposed to tuberculosis;
- with a history of an opportunistic infection;
- who have resided or traveled in areas of endemic tuberculosis or endemic mycoses, such as histoplasmosis, coccidioidomycosis, or blastomycosis; or
- with underlying conditions that may predispose them to infection.

Tuberculosis

Cases of reactivation of tuberculosis and new onset tuberculosis infections have been reported in patients receiving adalimumab products, including patients who have previously received treatment for latent or active tuberculosis. Reports included cases of pulmonary and extrapulmonary (i.e., disseminated) tuberculosis. Evaluate patients for tuberculosis risk factors and test for latent infection prior to initiating IDACIO and periodically during therapy.

Treatment of latent tuberculosis infection prior to therapy with TNF blocking agents has been shown to reduce the risk of tuberculosis reactivation during therapy. Prior to initiating IDACIO, assess if treatment for latent tuberculosis is needed; and consider an induration of ≥ 5 mm a positive tuberculin skin test result, even for patients previously vaccinated with Bacille Calmette-Guerin (BCG).

Consider anti-tuberculosis therapy prior to initiation of IDACIO in patients with a past history of latent or active tuberculosis in whom an adequate course of treatment cannot be confirmed, and for patients with a negative test for latent tuberculosis but having risk factors for tuberculosis infection. Despite prophylactic treatment for tuberculosis, cases of reactivated tuberculosis have occurred in patients treated with adalimumab products. Consultation with a physician with expertise in the treatment of tuberculosis is recommended to aid in the decision whether initiating anti- tuberculosis therapy is appropriate for an individual patient.

Strongly consider tuberculosis in the differential diagnosis in patients who develop a new infection during IDACIO treatment, especially in patients who have previously or recently traveled to countries with a high prevalence of tuberculosis, or who have had close contact with a person with active tuberculosis.

Monitoring

Closely monitor patients for the development of signs and symptoms of infection during and after treatment with IDACIO, including the development of tuberculosis in patients who tested negative for latent tuberculosis infection prior to initiating therapy. Tests for latent tuberculosis infection may also be falsely negative while on therapy with IDACIO.

Discontinue IDACIO if a patient develops a serious infection or sepsis. For a patient who develops a new infection during treatment with IDACIO, closely monitor them, perform a prompt and complete diagnostic workup appropriate for an immunocompromised patient, and initiate appropriate antimicrobial therapy.

Invasive Fungal Infections

If patients develop a serious systemic illness and they reside or travel in regions where mycoses are endemic, consider invasive fungal infection in the differential diagnosis. Antigen and antibody testing for histoplasmosis may be negative in some patients with active infection. Consider appropriate empiric antifungal therapy, taking into account both the risk for severe fungal infection and the risks of antifungal therapy, while a diagnostic workup is being performed. To aid in the management of such patients, consider consultation with a physician with expertise in the diagnosis and treatment of invasive fungal infections.

5.2 Malignancies

Consider the risks and benefits of TNF-blocker treatment including IDACIO prior to initiating therapy in patients with a known malignancy other than a successfully treated non-melanoma skin cancer (NMSC) or when considering continuing a TNF blocker in patients who develop a malignancy.

Malignancies in Adults

In the controlled portions of clinical trials of some TNF-blockers, including adalimumab products, more cases of malignancies have been observed among TNF-blocker-treated adult patients compared to control-treated adult patients. During the controlled portions of 39 global adalimumab clinical trials in adult patients with rheumatoid arthritis (RA), psoriatic arthritis (PsA), ankylosing spondylitis (AS), Crohn's disease (CD), ulcerative colitis (UC), plaque psoriasis (Ps), hidradenitis suppurativa (HS) and uveitis (UV), malignancies, other than non-melanoma (basal cell and squamous cell) skin cancer, were observed at a rate (95% confidence interval) of 0.7 (0.48, 1.03) per 100 patient-years among 7973 adalimumab-treated patients versus a rate of 0.7 (0.41, 1.17) per 100 patient-years among 4848 control-treated patients (median duration of treatment of 4 months for adalimumab-treated patients and 4 months for control-treated patients). In 52 global controlled and uncontrolled clinical trials of adalimumab in adult patients with RA, PsA, AS, CD, UC, Ps, HS, and UV, the most frequently observed malignancies, other than lymphoma and NMSC, were breast, colon, prostate, lung, and melanoma. The malignancies in adalimumab-treated patients in the controlled and uncontrolled portions of the studies were similar in type and number to what would be expected in the general U.S. population according to the SEER database (adjusted for age, gender, and race).^1

In controlled trials of other TNF blockers in adult patients at higher risk for malignancies (i.e., patients with COPD with a significant smoking history and cyclophosphamide-treated patients with Wegener's granulomatosis), a greater portion of malignancies occurred in the TNF blocker group compared to the control group.

Non-Melanoma Skin Cancer

During the controlled portions of 39 global adalimumab clinical trials in adult patients with RA, PsA, AS, CD, UC, Ps, HS, and UV, the rate (95% confidence interval) of NMSC was 0.8 (0.52, 1.09) per 100 patient-years among adalimumab-treated patients and 0.2 (0.10, 0.59) per 100 patient-years among control-treated patients. Examine all patients, and in particular patients with a medical history of prior prolonged immunosuppressant therapy or psoriasis patients with a history of PUVA treatment for the presence of NMSC prior to and during treatment with IDACIO.

Lymphoma and Leukemia

In the controlled portions of clinical trials of all the TNF-blockers in adults, more cases of lymphoma have been observed among TNF-blocker-treated patients compared to control-treated patients. In the controlled portions of 39 global adalimumab clinical trials in adult patients with RA, PsA, AS, CD, UC, Ps, HS, and UV, 2 lymphomas occurred among 7973 adalimumab-treated patients versus 1 among 4848 control-treated patients. In 52 global controlled and uncontrolled clinical trials of adalimumab in adult patients with RA, PsA, AS, CD, UC, Ps, HS, and UV with a median duration of approximately 0.7 years, including 24,605 patients and over 40,215 patient- years of adalimumab, the observed rate of lymphomas was approximately 0.11 per 100 patient- years. This is approximately 3-fold higher than expected in the general U.S. population according to the SEER database (adjusted for age, gender, and race).^1 Rates of lymphoma in clinical trials of adalimumab cannot be compared to rates of lymphoma in clinical trials of other TNF blockers and may not predict the rates observed in a broader patient population. Patients with RA and other chronic inflammatory diseases, particularly those with highly active disease and/or chronic exposure to immunosuppressant therapies, may be at a higher risk (up to several fold) than the general population for the development of lymphoma, even in the absence of TNF blockers. Post-marketing cases of acute and chronic leukemia have been reported in association with TNF-blocker use in RA and other indications. Even in the absence of TNF-blocker therapy, patients with RA may be at a higher risk (approximately 2-fold) than the general population for the development of leukemia.

Malignancies in Pediatric Patients and Young Adults

Malignancies, some fatal, have been reported among children, adolescents, and young adults who received treatment with TNF-blockers (initiation of therapy ≤ 18 years of age), of which IDACIO is a member. Approximately half the cases were lymphomas, including Hodgkin's and non-Hodgkin's lymphoma. The other cases represented a variety of different malignancies and included rare malignancies usually associated with immunosuppression and malignancies that are not usually observed in children and adolescents. The malignancies occurred after a median of 30 months of therapy (range 1 to 84 months). Most of the patients were receiving concomitant immunosuppressants. These cases were reported post-marketing and are derived from a variety of sources including registries and spontaneous postmarketing reports.

Postmarketing cases of hepatosplenic T-cell lymphoma (HSTCL), a rare type of T-cell lymphoma, have been reported in patients treated with TNF blockers including adalimumab products. These cases have had a very aggressive disease course and have been fatal. The majority of reported TNF blocker cases have occurred in patients with Crohn's disease or ulcerative colitis and the majority were in adolescent and young adult males. Almost all of these patients had received treatment with the immunosuppressants azathioprine or 6-mercaptopurine (6–MP) concomitantly with a TNF blocker at or prior to diagnosis. It is uncertain whether the occurrence of HSTCL is related to use of a TNF blocker or a TNF blocker in combination with these other immunosuppressants. The potential risk with the combination of azathioprine or 6-mercaptopurine and IDACIO should be carefully considered.

5.3 Hypersensitivity Reactions

Anaphylaxis and angioneurotic edema have been reported following administration of adalimumab products. If an anaphylactic or other serious allergic reaction occurs, immediately discontinue administration of IDACIO and institute appropriate therapy. In clinical trials of adalimumab, hypersensitivity reactions (e.g., rash, anaphylactoid reaction, fixed drug reaction, non-specified drug reaction, urticaria) have been observed.

5.4 Hepatitis B Virus Reactivation

Use of TNF blockers, including IDACIO, may increase the risk of reactivation of hepatitis B virus (HBV) in patients who are chronic carriers of this virus. In some instances, HBV reactivation occurring in conjunction with TNF blocker therapy has been fatal. The majority of these reports have occurred in patients concomitantly receiving other medications that suppress the immune system, which may also contribute to HBV reactivation. Evaluate patients at risk for HBV infection for prior evidence of HBV infection before initiating TNF blocker therapy. Exercise caution in prescribing TNF blockers for patients identified as carriers of HBV. Adequate data are not available on the safety or efficacy of treating patients who are carriers of HBV with anti-viral therapy in conjunction with TNF blocker therapy to prevent HBV reactivation. For patients who are carriers of HBV and require treatment with TNF blockers, closely monitor such patients for clinical and laboratory signs of active HBV infection throughout therapy and for several months following termination of therapy. In patients who develop HBV reactivation, stop IDACIO and initiate effective anti-viral therapy with appropriate supportive treatment. The safety of resuming TNF blocker therapy after HBV reactivation is controlled is not known. Therefore, exercise caution when considering resumption of IDACIO therapy in this situation and monitor patients closely.

5.5 Neurologic Reactions

Use of TNF blocking agents, including adalimumab products, has been associated with rare cases of new onset or exacerbation of clinical symptoms and/or radiographic evidence of central nervous system demyelinating disease, including multiple sclerosis (MS) and optic neuritis, and peripheral demyelinating disease, including Guillain-Barré syndrome. Exercise caution in considering the use of IDACIO in patients with preexisting or recent-onset central or peripheral nervous system demyelinating disorders; discontinuation of IDACIO should be considered if any of these disorders develop. There is a known association between intermediate uveitis and central demyelinating disorders.

5.6 Hematological Reactions

Rare reports of pancytopenia including aplastic anemia have been reported with TNF blocking agents. Adverse reactions of the hematologic system, including medically significant cytopenia (e.g., thrombocytopenia, leukopenia) have been infrequently reported with adalimumab products. The causal relationship of these reports to adalimumab products remains unclear. Advise all patients to seek immediate medical attention if they develop signs and symptoms suggestive of blood dyscrasias or infection (e.g., persistent fever, bruising, bleeding, pallor) while on IDACIO. Consider discontinuation of IDACIO therapy in patients with confirmed significant hematologic abnormalities.

5.7 Increased Risk of Infection when Used with Anakinra

Concurrent use of anakinra (an interleukin-1 antagonist) and another TNF-blocker, was associated with a greater proportion of serious infections and neutropenia and no added benefit compared with the TNF-blocker alone in patients with RA. Therefore, the combination of IDACIO and anakinra is not recommended [see Drug Interactions (7.2)].

5.8 Heart Failure

Cases of worsening congestive heart failure (CHF) and new onset CHF have been reported with TNF blockers. Cases of worsening CHF have also been observed with adalimumab products. Adalimumab products have not been formally studied in patients with CHF; however, in clinical trials of another TNF blocker, a higher rate of serious CHF-related adverse reactions was observed. Exercise caution when using IDACIO in patients who have heart failure and monitor them carefully.

5.9 Autoimmunity

Treatment with adalimumab products may result in the formation of autoantibodies and, rarely, in the development of a lupus-like syndrome. If a patient develops symptoms suggestive of a lupus-like syndrome following treatment with IDACIO, discontinue treatment [see Adverse Reactions (6.1)].

5.10 Immunizations

In a placebo-controlled clinical trial of patients with RA, no difference was detected in anti- pneumococcal antibody response between adalimumab and placebo treatment groups when the pneumococcal polysaccharide vaccine and influenza vaccine were administered concurrently with adalimumab. Similar proportions of patients developed protective levels of anti-influenza antibodies between adalimumab and placebo treatment groups; however, titers in aggregate to influenza antigens were moderately lower in patients receiving adalimumab. The clinical significance of this is unknown. Patients on IDACIO may receive concurrent vaccinations, except for live vaccines. No data are available on the secondary transmission of infection by live vaccines in patients receiving adalimumab products.

It is recommended that pediatric patients, if possible, be brought up to date with all immunizations in agreement with current immunization guidelines prior to initiating IDACIO therapy. Patients on IDACIO may receive concurrent vaccinations, except for live vaccines.

The safety of administering live or live-attenuated vaccines in infants exposed to adalimumab products in utero is unknown. Risks and benefits should be considered prior to vaccinating (live or live- attenuated) exposed infants [see Use in Specific Populations (8.1, 8.4)].

5.11 Increased Risk of Infection When Used with Abatacept

In controlled trials, the concurrent administration of TNF-blockers and abatacept was associated with a greater proportion of serious infections than the use of a TNF-blocker alone; the combination therapy, compared to the use of a TNF-blocker alone, has not demonstrated improved clinical benefit in the treatment of RA. Therefore, the combination of abatacept with TNF-blockers including IDACIO is not recommended [see Drug Interactions (7.2)].

6 ADVERSE REACTIONS

The following clinically significant adverse reactions are described elsewhere in the labeling:

- Serious Infections [see Warnings and Precautions (5.1)]
- Malignancies [see Warnings and Precautions (5.2)]
- Hypersensitivity Reactions [see Warnings and Precautions (5.3)]
- Hepatitis B Virus Reactivation [see Warnings and Precautions (5.4)]
- Neurologic Reactions [see Warnings and Precautions (5.5)]
- Hematological Reactions [see Warnings and Precautions (5.6)]
- Heart Failure [see Warnings and Precautions (5.8)]
- Autoimmunity [see Warnings and Precautions (5.9)]

6.1 Clinical Trials Experience

Because clinical trials are conducted under widely varying conditions, adverse reaction rates observed in the clinical trials of a drug cannot be directly compared to rates in the clinical trials of another drug and may not reflect the rates observed in practice.

The most common adverse reaction with adalimumab was injection site reactions. In placebo- controlled trials, 20% of patients treated with adalimumab developed injection site reactions (erythema and/or itching, hemorrhage, pain or swelling), compared to 14% of patients receiving placebo. Most injection site reactions were described as mild and generally did not necessitate drug discontinuation.

The proportion of patients who discontinued treatment due to adverse reactions during the double-blind, placebo-controlled portion of studies in patients with RA (i.e., Studies RA-I, RA- II, RA-III and RA-IV) was 7% for patients taking adalimumab and 4% for placebo-treated patients. The most common adverse reactions leading to discontinuation of adalimumab in these RA studies were clinical flare reaction (0.7%), rash (0.3%) and pneumonia (0.3%).

Infections

In the controlled portions of the 39 global adalimumab clinical trials in adult patients with RA, PsA, AS, CD, UC, Ps, HS and UV, the rate of serious infections was 4.3 per 100 patient-years in 7973 adalimumab-treated patients versus a rate of 2.9 per 100 patient-years in 4848 control-treated patients. Serious infections observed included pneumonia, septic arthritis, prosthetic and post- surgical infections, erysipelas, cellulitis, diverticulitis, and pyelonephritis [see Warnings and Precautions (5.1)].

Tuberculosis and Opportunistic Infections

In 52 global controlled and uncontrolled clinical trials in RA, PsA, AS, CD, UC, Ps, HS, and UV that included 24,605 adalimumab-treated patients, the rate of reported active tuberculosis was 0.20 per 100 patient-years and the rate of positive PPD conversion was 0.09 per 100 patient-years. In a subgroup of 10,113 U.S. and Canadian adalimumab-treated patients, the rate of reported active TB was 0.05 per 100 patient-years and the rate of positive PPD conversion was 0.07 per 100 patient-years. These trials included reports of miliary, lymphatic, peritoneal, and pulmonary TB. Most of the TB cases occurred within the first eight months after initiation of therapy and may reflect recrudescence of latent disease. In these global clinical trials, cases of serious opportunistic infections have been reported at an overall rate of 0.05 per 100 patient-years. Some cases of serious opportunistic infections and TB have been fatal [see Warnings and Precautions (5.1)].

Autoantibodies

In the rheumatoid arthritis controlled trials, 12% of patients treated with adalimumab and 7% of placebo-treated patients that had negative baseline ANA titers developed positive titers at week 24. Two patients out of 3046 treated with adalimumab developed clinical signs suggestive of new- onset lupus-like syndrome. The patients improved following discontinuation of therapy. No patients developed lupus nephritis or central nervous system symptoms. The impact of long-term treatment with adalimumab products on the development of autoimmune diseases is unknown.

Liver Enzyme Elevations

There have been reports of severe hepatic reactions including acute liver failure in patients receiving TNF-blockers. In controlled Phase 3 trials of adalimumab (40 mg SC every other week) in patients with RA, PsA, and AS with control period duration ranging from 4 to 104 weeks, ALT elevations ≥ 3 x ULN occurred in 3.5% of adalimumab-treated patients and 1.5% of control- treated patients. Since many of these patients in these trials were also taking medications that cause liver enzyme elevations (e.g., NSAIDS, MTX), the relationship between adalimumab and the liver enzyme elevations is not clear. In a controlled Phase 3 trial of adalimumab in patients with polyarticular JIA who were 4 to 17 years, ALT elevations ≥ 3 x ULN occurred in 4.4% of adalimumab-treated patients and 1.5% of control-treated patients (ALT more common than AST); liver enzyme test elevations were more frequent among those treated with the combination of adalimumab and MTX than those treated with adalimumab alone. In general, these elevations did not lead to discontinuation of adalimumab treatment. No ALT elevations ≥ 3 x ULN occurred in the open-label study of adalimumab in patients with polyarticular JIA who were 2 to <4 years.

In controlled Phase 3 trials of adalimumab (initial doses of 160 mg and 80 mg, or 80 mg and 40 mg on Days 1 and 15, respectively, followed by 40 mg every other week) in adult patients with Crohn's Disease with a control period duration ranging from 4 to 52 weeks, ALT elevations ≥ 3 x ULN occurred in 0.9% of adalimumab-treated patients and 0.9% of control-treated patients. In the Phase 3 trial of adalimumab in pediatric patients with Crohn's disease which evaluated efficacy and safety of two body weight based maintenance dose regimens following body weight based induction therapy up to 52 weeks of treatment, ALT elevations ≥ 3 x ULN occurred in 2.6% (5/192) of patients, of whom 4 were receiving concomitant immunosuppressants at baseline; none of these patients discontinued due to abnormalities in ALT tests. In controlled Phase 3 trials of adalimumab (initial doses of 160 mg and 80 mg on Days 1 and 15 respectively, followed by 40 mg every other week) in adult patients with UC with control period duration ranging from 1 to 52 weeks, ALT elevations ≥3 x ULN occurred in 1.5% of adalimumab-treated patients and 1.0% of control-treated patients. In controlled Phase 3 trials of adalimumab (initial dose of 80 mg then 40 mg every other week) in patients with Ps with control period duration ranging from 12 to 24 weeks, ALT elevations ≥ 3 x ULN occurred in 1.8% of adalimumab-treated patients and 1.8% of control-treated patients. In controlled trials of adalimumab (initial doses of 160 mg at Week 0 and 80 mg at Week 2, followed by 40 mg every week starting at Week 4), in subjects with HS with a control period duration ranging from 12 to 16 weeks, ALT elevations ≥ 3 x ULN occurred in 0.3% of adalimumab-treated subjects and 0.6% of control-treated subjects. In controlled trials of adalimumab (initial doses of 80 mg at Week 0 followed by 40 mg every other week starting at Week 1) in adult patients with uveitis with an exposure of 165.4 PYs and 119.8 PYs in adalimumab-treated and control-treated patients, respectively, ALT elevations ≥ 3 x ULN occurred in 2.4% of adalimumab-treated patients and 2.4% of control-treated patients.

Other Adverse Reactions

Rheumatoid Arthritis Clinical Studies

The data described below reflect exposure to adalimumab in 2468 patients, including 2073 exposed for 6 months, 1497 exposed for greater than one year and 1380 in adequate and well-controlled studies (Studies RA-I, RA-II, RA-III, and RA-IV). Adalimumab was studied primarily in placebo- controlled trials and in long-term follow up studies for up to 36 months duration. The population had a mean age of 54 years, 77% were female, 91% were Caucasian and had moderately to severely active rheumatoid arthritis. Most patients received 40 mg adalimumab every other week [see Clinical Studies (14.1)].

Table 1 summarizes reactions reported at a rate of at least 5% in patients treated with adalimumab 40 mg every other week compared to placebo and with an incidence higher than placebo. In Study RA-III, the types and frequencies of adverse reactions in the second year open-label extension were similar to those observed in the one-year double-blind portion.

Table 1. Adverse Reactions Reported by ≥5% of Patients Treated with Adalimumab during Placebo-Controlled Period of Pooled RA Studies (Studies RA-I, RA-II, RA-III, and RA-IV)
 | Adalimumab 40 mg subcutaneous Every Other Week | Placebo
 | (N=705) | (N=690)
Adverse Reaction (Preferred Term)
Respiratory
Upper respiratory infection | 17% | 13%
Sinusitis | 11% | 9%
Flu syndrome | 7% | 6%
Gastrointestinal
Nausea | 9% | 8%
Abdominal pain | 7% | 4%
Laboratory Tests*
Laboratory test abnormal | 8% | 7%
Hypercholesterolemia | 6% | 4%
Hyperlipidemia | 7% | 5%
Hematuria | 5% | 4%
Alkaline phosphatase increased | 5% | 3%
Other
Headache | 12% | 8%
Rash | 12% | 6%
Accidental injury | 10% | 8%
Injection site reaction ** | 8% | 1%
Back pain | 6% | 4%
Urinary tract infection | 8% | 5%
Hypertension | 5% | 3%
* Laboratory test abnormalities were reported as adverse reactions in European trials
** Does not include injection site erythema, itching, hemorrhage, pain or swelling

Less Common Adverse Reactions in Rheumatoid Arthritis Clinical Studies

Other infrequent serious adverse reactions that do not appear in the Warnings and Precautions or Adverse Reaction sections that occurred at an incidence of less than 5% in adalimumab-treated patients in RA studies were:

Body As A Whole: Pain in extremity, pelvic pain, surgery, thorax pain

Cardiovascular System: Arrhythmia, atrial fibrillation, chest pain, coronary artery disorder, heart arrest, hypertensive encephalopathy, myocardial infarct, palpitation, pericardial effusion, pericarditis, syncope, tachycardia

Digestive System: Cholecystitis, cholelithiasis, esophagitis, gastroenteritis, gastrointestinal hemorrhage, hepatic necrosis, vomiting

Endocrine System: Parathyroid disorder

Hemic And Lymphatic System: Agranulocytosis, polycythemia

Metabolic And Nutritional Disorders: Dehydration, healing abnormal, ketosis, paraproteinemia, peripheral edema

Musculo-Skeletal System: Arthritis, bone disorder, bone fracture (not spontaneous), bone necrosis, joint disorder, muscle cramps, myasthenia, pyogenic arthritis, synovitis, tendon disorder

Neoplasia: Adenoma

Nervous System: Confusion, paresthesia, subdural hematoma, tremor

Respiratory System: Asthma, bronchospasm, dyspnea, lung function decreased, pleural effusion

Special Senses: Cataract

Thrombosis: Thrombosis leg

Urogenital System: Cystitis, kidney calculus, menstrual disorder

Juvenile Idiopathic Arthritis Clinical Studies

In general, the adverse reactions in the adalimumab-treated patients in the polyarticular juvenile idiopathic arthritis (JIA) trials (Studies JIA-I and JIA-II) [see Clinical Studies (14.2)] were similar in frequency and type to those seen in adult patients [see Warnings and Precautions (5), Adverse Reactions (6)]. Important findings and differences from adults are discussed in the following paragraphs.

In Study JIA-I, adalimumab was studied in 171 patients who were 4 to 17 years of age, with polyarticular JIA. Severe adverse reactions reported in the study included neutropenia, streptococcal pharyngitis, increased aminotransferases, herpes zoster, myositis, metrorrhagia, and appendicitis. Serious infections were observed in 4% of patients within approximately 2 years of initiation of treatment with adalimumab and included cases of herpes simplex, pneumonia, urinary tract infection, pharyngitis, and herpes zoster.

In Study JIA-I, 45% of patients experienced an infection while receiving adalimumab with or without concomitant MTX in the first 16 weeks of treatment. The types of infections reported in adalimumab-treated patients were generally similar to those commonly seen in polyarticular JIA patients who are not treated with TNF blockers. Upon initiation of treatment, the most common adverse reactions occurring in this patient population treated with adalimumab were injection site pain and injection site reaction (19% and 16%, respectively). A less commonly reported adverse event in patients receiving adalimumab was granuloma annulare which did not lead to discontinuation of adalimumab treatment.

In the first 48 weeks of treatment in Study JIA-I, non-serious hypersensitivity reactions were seen in approximately 6% of patients and included primarily localized allergic hypersensitivity reactions and allergic rash.

In Study JIA-I, 10% of patients treated with adalimumab who had negative baseline anti-dsDNA antibodies developed positive titers after 48 weeks of treatment. No patient developed clinical signs of autoimmunity during the clinical trial.

Approximately 15% of patients treated with adalimumab developed mild-to-moderate elevations of creatine phosphokinase (CPK) in Study JIA-I. Elevations exceeding 5 times the upper limit of normal were observed in several patients. CPK concentrations decreased or returned to normal in all patients. Most patients were able to continue adalimumab without interruption.

In Study JIA-II, adalimumab was studied in 32 patients who were 2 to <4 years of age or 4 years of age and older weighing <15 kg with polyarticular JIA. The safety profile for this patient population was similar to the safety profile seen in patients 4 to 17 years of age with polyarticular JIA.

In Study JIA-II, 78% of patients experienced an infection while receiving adalimumab. These included nasopharyngitis, bronchitis, upper respiratory tract infection, otitis media, and were mostly mild to moderate in severity. Serious infections were observed in 9% of patients receiving adalimumab in the study and included dental caries, rotavirus gastroenteritis, and varicella.

In Study JIA-II, non-serious allergic reactions were observed in 6% of patients and included intermittent urticaria and rash, which were all mild in severity.

Psoriatic Arthritis and Ankylosing Spondylitis Clinical Studies

Adalimumab has been studied in 395 patients with psoriatic arthritis (PsA) in two placebo- controlled trials and in an open label study and in 393 patients with ankylosing spondylitis (AS) in two placebo-controlled studies [see Clinical Studies (14.3, 14.4)]. The safety profile for patients with PsA and AS treated with adalimumab 40 mg every other week was similar to the safety profile seen in patients with RA, adalimumab Studies RA-I through IV.

Crohn's Disease Clinical Studies

Adults: The safety profile of adalimumab in 1478 adult patients with Crohn's disease from four placebo-controlled and two open-label extension studies [see Clinical Studies (14.5)] was similar to the safety profile seen in patients with RA.

Pediatric Patients 6 Years to 17 Years: The safety profile of adalimumab in 192 pediatric patients from one double-blind study (Study PCD-I) and one open-label extension study [see Clinical Studies (14.6)] was similar to the safety profile seen in adult patients with Crohn's disease.

During the 4-week open label induction phase of Study PCD-I, the most common adverse reactions occurring in the pediatric population treated with adalimumab were injection site pain and injection site reaction (6% and 5%, respectively).

A total of 67% of children experienced an infection while receiving adalimumab in Study PCD-I. These included upper respiratory tract infection and nasopharyngitis.

A total of 5% of children experienced a serious infection while receiving adalimumab in Study PCD-I. These included viral infection, device related sepsis (catheter), gastroenteritis, H1N1 influenza, and disseminated histoplasmosis.

In Study PCD-I, allergic reactions were observed in 5% of children which were all non-serious and were primarily localized reactions.

Ulcerative Colitis Clinical Studies

Adults: The safety profile of adalimumab in 1010 adult patients with ulcerative colitis (UC) from two placebo-controlled studies and one open-label extension study [see Clinical Studies (14.7)] was similar to the safety profile seen in patients with RA.

Plaque Psoriasis Clinical Studies

Adalimumab has been studied in 1696 subjects with plaque psoriasis (Ps) in placebo-controlled and open-label extension studies [see Clinical Studies (14.8)]. The safety profile for subjects with Ps treated with adalimumab was similar to the safety profile seen in subjects with RA with the following exceptions. In the placebo-controlled portions of the clinical trials in Ps subjects, adalimumab-treated subjects had a higher incidence of arthralgia when compared to controls (3% vs. 1%).

Hidradenitis Suppurativa Clinical Studies

Adalimumab has been studied in 727 subjects with hidradenitis suppurativa (HS) in three placebo- controlled studies and one open-label extension study [see Clinical Studies (14.9)]. The safety profile for subjects with HS treated with adalimumab weekly was consistent with the known safety profile of adalimumab.

Flare of HS, defined as ≥25% increase from baseline in abscesses and inflammatory nodule counts and with a minimum of 2 additional lesions, was documented in 22 (22%) of the 100 subjects who were withdrawn from adalimumab treatment following the primary efficacy timepoint in two studies.

Uveitis Clinical Studies

Adalimumab has been studied in 464 adult patients with uveitis (UV) in placebo-controlled and open-label extension studies (Study PUV-I) [see Clinical Studies (14.10)]. The safety profile for patients with UV treated with adalimumab was similar to the safety profile seen in patients with RA.

6.2 Immunogenicity

The observed incidence of anti-drug antibodies is highly dependent on the sensitivity and specificity of the assay. Differences in assay methods preclude meaningful comparisons of the incidence of anti-drug antibodies in the studies described below with the incidence of anti-drug antibodies in other studies, including those of adalimumab or of other adalimumab products.

There are two assays that have been used to measure anti-adalimumab antibodies. With the ELISA, antibodies to adalimumab could be detected only when serum adalimumab concentrations were < 2 mcg/mL. The ECL assay can detect anti-adalimumab antibody titers independent of adalimumab concentrations in the serum samples. The incidence of anti-adalimumab antibody (AAA) development in patients treated with adalimumab are presented in Table 2.

Table 2: Anti-Adalimumab Antibody Development Determined by ELISA and ECL Assay in Patients Treated with adalimumab
Indications |  | Study Duration | Anti-Adalimumab Antibody Incidence by ELISA (n/N) |  | Anti-Adalimumab Antibody Incidence by ECL Assay (n/N)
Indications |  | Study Duration | In all patients who received adalimumab | In patients with serum adalimumab concentrations < 2 mcg/mL
Rheumatoid Arthritisa |  | 6 to 12 months | 5% (58/1062) | NR | NA
Juvenile Idiopathic Arthritis (JIA) | 4 to 17 years of ageb | 48 weeks | 16% (27/171) | NR | NA
Juvenile Idiopathic Arthritis (JIA) | 2 to 4 years of age or ≥ 4 years of age and weighing < 15 kg | 24 weeks | 7% (1/15)c | NR | NA
Psoriatic Arthritisd |  | 48 weekse | 13% (24/178) | NR | NA
Ankylosing Spondylitis |  | 24 weeks | 9% (16/185) | NR | NA
Adult Crohn's Disease |  | 56 weeks | 3% (7/269) | 8% (7/86) | NA
Pediatric Crohn's Disease |  | 52 weeks | 3% (6/182) | 10% (6/58) | NA
Adult Ulcerative Colitis |  | 52 weeks | 5% (19/360) | 21% (19/92) | NA
Plaque Psoriasisf |  | Up to 52 weeksg | 8% (77/920) | 21% (77/372) | NA
Hidradenitis Suppurativa |  | 36 weeks | 7% (30/461) | 28% (58/207)h | 61% (272/445)i
Non-infectious Uveitis |  | 52 weeks | 5% (12/249) | 21% (12/57) | 40% (99/249) j
n: number of patients with anti-adalimumab antibody; NR: not reported; NA: Not applicable (not performed)
a In patients receiving concomitant methotrexate (MTX), the incidence of anti-adalimumab antibody was 1% compared to 12% with adalimumab monotherapy
b In patients receiving concomitant MTX, the incidence of anti-adalimumab antibody was 6% compared to 26% with adalimumab monotherapy
c This patient received concomitant MTX
d In patients receiving concomitant MTX, the incidence of antibody development was 7% compared to 1% in RA
e Subjects enrolled after completing 2 previous studies of 24 weeks or 12 weeks of treatments.
f In plaque psoriasis patients who were on adalimumab monotherapy and subsequently withdrawn from the treatment, the rate of antibodies to adalimumab after retreatment was similar to the rate observed prior to withdrawal
g One 12-week Phase 2 study and one 52-week Phase 3 study
h Among subjects in the 2 Phase 3 studies who stopped adalimumab treatment for up to 24 weeks and in whom adalimumab serum levels subsequently declined to <2 mcg/mL (approximately 22% of total subjects studied)
i No apparent association between antibody development and safety was observed
j No correlation of antibody development to safety or efficacy outcomes was observed

Rheumatoid Arthritis and Psoriatic Arthritis: Patients in Studies RA-I, RA-II, and RA-III were tested at multiple time points for antibodies to adalimumab using the ELISA during the 6- to 12-month period. No apparent correlation of antibody development to adverse reactions was observed. With monotherapy, patients receiving every other week dosing may develop antibodies more frequently than those receiving weekly dosing. In patients receiving the recommended dosage of 40 mg every other week as monotherapy, the ACR 20 response was lower among antibody-positive patients than among antibody-negative patients. The long-term immunogenicity of adalimumab products is unknown.

6.3 Postmarketing Experience

The following adverse reactions have been identified during post-approval use of adalimumab products. Because these reactions are reported voluntarily from a population of uncertain size, it is not always possible to reliably estimate their frequency or establish a causal relationship to adalimumab products exposure.

Gastrointestinal disorders: Diverticulitis, large bowel perforations including perforations associated with diverticulitis and appendiceal perforations associated with appendicitis, pancreatitis

General disorders and administration site conditions: Pyrexia

Hepato-biliary disorders: Liver failure, hepatitis

Immune system disorders: Sarcoidosis

Neoplasms benign, malignant and unspecified (including cysts and polyps): Merkel Cell Carcinoma (neuroendocrine carcinoma of the skin)

Nervous system disorders: Demyelinating disorders (e.g., optic neuritis, Guillain-Barré syndrome), cerebrovascular accident

Respiratory disorders: Interstitial lung disease, including pulmonary fibrosis, pulmonary embolism

Skin reactions: Stevens Johnson Syndrome, cutaneous vasculitis, erythema multiforme, new or worsening psoriasis (all sub-types including pustular and palmoplantar), alopecia, lichenoid skin reaction

Vascular disorders: Systemic vasculitis, deep vein thrombosis

7 DRUG INTERACTIONS

7.1 Methotrexate

Adalimumab has been studied in rheumatoid arthritis (RA) patients taking concomitant methotrexate (MTX). Although MTX reduced the apparent adalimumab clearance, the data do not suggest the need for dose adjustment of either IDACIO or MTX [see Clinical Pharmacology (12.3)].

7.2 Biological Products

In clinical studies in patients with RA, an increased risk of serious infections has been observed with the combination of TNF blockers with anakinra or abatacept, with no added benefit; therefore, use of IDACIO with abatacept or anakinra is not recommended in patients with RA [see Warnings and Precautions (5.7, 5.11)]. A higher rate of serious infections has also been observed in patients with RA treated with rituximab who received subsequent treatment with a TNF blocker. There is insufficient information regarding the concomitant use of IDACIO and other biologic products for the treatment of RA, PsA, AS, CD, UC, Ps, HS and UV. Concomitant administration of IDACIO with other biologic DMARDS (e.g., anakinra and abatacept) or other TNF blockers is not recommended based upon the possible increased risk for infections and other potential pharmacological interactions.

7.3 Live Vaccines

Avoid the use of live vaccines with IDACIO [see Warnings and Precautions (5.10)].

7.4 Cytochrome P450 Substrates

The formation of CYP450 enzymes may be suppressed by increased concentrations of cytokines (e.g., TNFα, IL-6) during chronic inflammation. It is possible for products that antagonize cytokine activity, such as adalimumab products, to influence the formation of CYP450 enzymes. Upon initiation or discontinuation of IDACIO in patients being treated with CYP450 substrates with a narrow therapeutic index, monitoring of the effect (e.g., warfarin) or drug concentration (e.g., cyclosporine or theophylline) is recommended and the individual dose of the drug product may be adjusted as needed.

8 USE IN SPECIFIC POPULATIONS

8.1 Pregnancy

Risk Summary

Available studies with use of adalimumab during pregnancy do not reliably establish an association between adalimumab and major birth defects. Clinical data are available from the Organization of Teratology Information Specialists (OTIS)/MotherToBaby Pregnancy Registry in pregnant women with rheumatoid arthritis (RA) or Crohn's disease (CD) treated with adalimumab. Registry results showed a rate of 10% for major birth defects with first trimester use of adalimumab in pregnant women with RA or CD and a rate of 7.5% for major birth defects in the disease-matched comparison cohort. The lack of pattern of major birth defects is reassuring and differences between exposure groups may have impacted the occurrence of birth defects (see Data).

Adalimumab is actively transferred across the placenta during the third trimester of pregnancy and may affect immune response in the in-utero exposed infant (see Clinical Considerations). In an embryo-fetal perinatal development study conducted in cynomolgus monkeys, no fetal harm or malformations were observed with intravenous administration of adalimumab during organogenesis and later in gestation, at doses that produced exposures up to approximately 373 times the maximum recommended human dose (MRHD) of 40 mg subcutaneous without methotrexate (see Data).

The estimated background risk of major birth defects and miscarriage for the indicated populations is unknown. All pregnancies have a background risk of birth defect, loss, or other adverse outcomes. In the U.S. general population, the estimated background risk of major birth defects and miscarriage in clinically recognized pregnancies is 2-4% and 15-20%, respectively.

Clinical Considerations

Disease-associated maternal and embryo/fetal risk

Published data suggest that the risk of adverse pregnancy outcomes in women with RA or inflammatory bowel disease (IBD) is associated with increased disease activity. Adverse pregnancy outcomes include preterm delivery (before 37 weeks of gestation), low birth weight (less than 2500 g) infants, and small for gestational age at birth.

Fetal/Neonatal Adverse Reactions

Monoclonal antibodies are increasingly transported across the placenta as pregnancy progresses, with the largest amount transferred during the third trimester (see Data). Risks and benefits should be considered prior to administering live or live-attenuated vaccines to infants exposed to adalimumab products in utero [see Use in Specific Populations (8.4)].

Data

Human Data

A prospective cohort pregnancy exposure registry conducted by OTIS/MotherToBaby in the U.S. and Canada between 2004 and 2016 compared the risk of major birth defects in live-born infants of 221 women (69 RA, 152 CD) treated with adalimumab during the first trimester and 106 women (74 RA, 32 CD) not treated with adalimumab.

The proportion of major birth defects among live-born infants in the adalimumab-treated and untreated cohorts was 10% (8.7% RA, 10.5% CD) and 7.5% (6.8% RA, 9.4% CD), respectively. The lack of pattern of major birth defects is reassuring and differences between exposure groups may have impacted the occurrence of birth defects. This study cannot reliably establish whether there is an association between adalimumab and major birth defects because of methodological limitations of the registry, including small sample size, the voluntary nature of the study, and the non-randomized design.

In an independent clinical study conducted in ten pregnant women with IBD treated with adalimumab, adalimumab concentrations were measured in maternal serum as well as in cord blood (n=10) and infant serum (n=8) on the day of birth. The last dose of adalimumab was given between 1 and 56 days prior to delivery. Adalimumab concentrations were 0.16-19.7 mcg/mL in cord blood, 4.28-17.7 mcg/mL in infant serum, and 0-16.1 mcg/mL in maternal serum. In all but one case, the cord blood concentration of adalimumab was higher than the maternal serum concentration, suggesting adalimumab actively crosses the placenta. In addition, one infant had serum concentrations at each of the following: 6 weeks (1.94 mcg/mL), 7 weeks (1.31 mcg/mL), 8 weeks (0.93 mcg/mL), and 11 weeks (0.53 mcg/mL), suggesting adalimumab can be detected in the serum of infants exposed in utero for at least 3 months from birth.

Animal Data

In an embryo-fetal perinatal development study, pregnant cynomolgus monkeys received adalimumab from gestation days 20 to 97 at doses that produced exposures up to 373 times that achieved with the MRHD without methotrexate (on an AUC basis with maternal IV doses up to 100 mg/kg/week). Adalimumab did not elicit harm to the fetuses or malformations.

8.2 Lactation

Risk Summary

Limited data from case reports in the published literature describe the presence of adalimumab in human milk at infant doses of 0.1% to 1% of the maternal serum concentration. Published data suggest that the systemic exposure to a breastfed infant is expected to be low because adalimumab is a large molecule and is degraded in the gastrointestinal tract. However, the effects of local exposure in the gastrointestinal tract are unknown. There are no reports of adverse effects of adalimumab products on the breastfed infant and no effects on milk production. The developmental and health benefits of breastfeeding should be considered along with the mother's clinical need for IDACIO and any potential adverse effects on the breastfed child from IDACIO or from the underlying maternal condition.

8.4 Pediatric Use

The safety and effectiveness of IDACIO have been established for:

- reducing signs and symptoms of moderately to severely active polyarticular JIA in pediatric patients 2 years of age and older.
- the treatment of moderately to severely active Crohn's disease in pediatric patients 6 years of age and older.

Pediatric assessments for IDACIO demonstrate that IDACIO is safe and effective for pediatric patients in indications for which HUMIRA (adalimumab) is approved. However, IDACIO is not approved for such indications due to marketing exclusivity for HUMIRA (adalimumab).

Due to their inhibition of TNFα, adalimumab products administered during pregnancy could affect immune response in the in utero-exposed newborn and infant. Data from eight infants exposed to adalimumab in utero suggest adalimumab crosses the placenta [see Use in Specific Populations (8.1)]. The clinical significance of elevated adalimumab concentrations in infants is unknown. The safety of administering live or live-attenuated vaccines in exposed infants is unknown. Risks and benefits should be considered prior to vaccinating (live or live-attenuated) exposed infants.

Post-marketing cases of lymphoma, including hepatosplenic T-cell lymphoma and other malignancies, some fatal, have been reported among children, adolescents, and young adults who received treatment with TNF-blockers including adalimumab products [see Warnings and Precautions (5.2)].

Juvenile Idiopathic Arthritis

In Study JIA-I, adalimumab was shown to reduce signs and symptoms of active polyarticular JIA in patients 4 to 17 years of age [see Clinical Studies (14.2)]. In Study JIA-II, the safety profile for patients 2 to <4 years of age was similar to the safety profile for patients 4 to 17 years of age with polyarticular JIA [see Adverse Reactions (6.1)]. Adalimumab products have not been studied in patients with polyarticular JIA less than 2 years of age or in patients with a weight below 10 kg.

The safety of adalimumab in patients in the polyarticular JIA trials was generally similar to that observed in adults with certain exceptions [see Adverse Reactions (6.1)].

The safety and effectiveness of IDACIO have not been established in pediatric patients with JIA less than 2 years of age.

Pediatric Crohn's Disease

The safety and effectiveness of IDACIO for the treatment of moderately to severely active Crohn's disease have been established in pediatric patients 6 years of age and older. Use of IDACIO for this indication is supported by IDACIO's approval as a biosimilar to adalimumab and evidence from adequate and well-controlled studies in adults with additional data of adalimumab from a randomized, double-blind, 52-week clinical study of two dose concentrations of adalimumab in 192 pediatric patients (6 years to 17 years of age) [see Adverse Reactions (6.1), Clinical Pharmacology (12.2, 12.3), Clinical Studies (14.6)]. The adverse reaction profile in patients 6 years to 17 years of age was similar to adults.

The safety and effectiveness of IDACIO have not been established in pediatric patients with Crohn's disease less than 6 years of age.

8.5 Geriatric Use

A total of 519 RA patients 65 years of age and older, including 107 patients 75 years of age and older, received adalimumab in clinical studies RA-I through IV. No overall difference in effectiveness was observed between these patients and younger patients. The frequency of serious infection and malignancy among adalimumab treated patients 65 years of age and older was higher than for those less than 65 years of age. Consider the benefits and risks of IDACIO in patients 65 years of age and older. In patients treated with IDACIO, closely monitor for the development of infection or malignancy [see Warnings and Precautions (5.1, 5.2)].

10 OVERDOSAGE

Doses up to 10 mg/kg have been administered to patients in clinical trials without evidence of dose-limiting toxicities. In case of overdosage, it is recommended that the patient be monitored for any signs or symptoms of adverse reactions or effects and appropriate symptomatic treatment instituted immediately.

11 DESCRIPTION

Adalimumab-aacf is a tumor necrosis factor blocker. Adalimumab-aacf is a recombinant human IgG1 monoclonal antibody created using phage display technology resulting in an antibody with human derived heavy and light chain variable regions and human IgG1:k constant regions. Adalimumab-aacf is produced by recombinant DNA technology in a mammalian cell (Chinese Hamster Ovary (CHO)) expression system and is purified by a process that includes specific viral inactivation and removal steps. It consists of 1330 amino acids and has a molecular weight of approximately 148 kilodaltons.

IDACIO (adalimumab-aacf) injection is supplied as a sterile, preservative-free solution for subcutaneous administration. The drug product is supplied as either a single-dose, prefilled pen (IDACIO Pen), as a single-dose, 1 mL or prefilled glass syringe or as a single dose institutional use vial kit. Enclosed within the pen is a single-dose, 1 mL prefilled glass syringe. The solution of IDACIO is clear and colorless to pale yellow, with a pH of about 5.2.

Each 40 mg/0.8 mL prefilled syringe or prefilled pen, or institutional use vial kit delivers 0.8 mL (40 mg) of drug product. Each 0.8 mL of IDACIO contains adalimumab-aacf (40 mg) and glacial acetic acid (0.5 mg), trehalose (54.8 mg), polysorbate 80 (0.8 mg), sodium chloride (2.3 mg), and Water for Injection. Sodium hydroxide is added to adjust pH.

12 CLINICAL PHARMACOLOGY

12.1 Mechanism of Action

Adalimumab products bind specifically to TNF-alpha and block its interaction with the p55 and p75 cell surface TNF receptors. Adalimumab products also lyse surface TNF expressing cells in vitro in the presence of complement. Adalimumab products do not bind or inactivate lymphotoxin (TNF-beta). TNF is a naturally occurring cytokine that is involved in normal inflammatory and immune responses. Elevated concentrations of TNF are found in the synovial fluid of patients with RA, JIA, PsA, and AS and play an important role in both the pathologic inflammation and the joint destruction that are hallmarks of these diseases. Increased concentrations of TNF are also found in psoriasis plaques. In Ps, treatment with IDACIO may reduce the epidermal thickness and infiltration of inflammatory cells. The relationship between these pharmacodynamic activities and the mechanism(s) by which adalimumab products exert their clinical effects is unknown.

Adalimumab products also modulate biological responses that are induced or regulated by TNF, including changes in the concentrations of adhesion molecules responsible for leukocyte migration (ELAM-1, VCAM-1, and ICAM-1 with an IC50 of 1-2 X 10^-10M).

12.2 Pharmacodynamics

After treatment with adalimumab, a decrease in concentrations of acute phase reactants of inflammation (C-reactive protein [CRP] and erythrocyte sedimentation rate [ESR]) and serum cytokines (IL-6) was observed compared to baseline in patients with rheumatoid arthritis. A decrease in CRP concentrations was also observed in patients with Crohn's disease, ulcerative colitis and hidradenitis suppurativa. Serum concentrations of matrix metalloproteinases (MMP-1 and MMP-3) that produce tissue remodeling responsible for cartilage destruction were also decreased after adalimumab administration.

12.3 Pharmacokinetics

The pharmacokinetics of adalimumab were linear over the dose range of 0.5 to 10 mg/kg following administration of a single intravenous dose (adalimumab products are not approved for intravenous use). Following 20, 40, and 80 mg every other week and every week subcutaneous administration, adalimumab mean serum trough concentrations at steady state increased approximately proportionally with dose in RA patients. The mean terminal half-life was approximately 2 weeks, ranging from 10 to 20 days across studies. Healthy subjects and patients with RA displayed similar adalimumab pharmacokinetics.

Adalimumab exposure in patients treated with 80 mg every other week is estimated to be comparable with that in patients treated with 40 mg every week.

Absorption

The average absolute bioavailability of adalimumab following a single 40 mg subcutaneous dose was 64%. The mean time to reach the maximum concentration was 5.5 days (131 ± 56 hours) and the maximum serum concentration was 4.7 ± 1.6 mcg/mL in healthy subjects following a single 40 mg subcutaneous administration of adalimumab.

Distribution

The distribution volume (Vss) ranged from 4.7 to 6.0 L following intravenous administration of doses ranging from 0.25 to 10 mg/kg in RA patients.

Elimination

The single dose pharmacokinetics of adalimumab in RA patients were determined in several studies with intravenous doses ranging from 0.25 to 10 mg/kg. The systemic clearance of adalimumab is approximately 12 mL/hr. In long-term studies with dosing more than two years, there was no evidence of changes in clearance over time in RA patients.

Patient Population

Rheumatoid Arthritis and Ankylosing Spondylitis: In patients receiving 40 mg adalimumab every other week, adalimumab mean steady-state trough concentrations were approximately 5 mcg/mL and 8 to 9 mcg/mL, without and with MTX concomitant treatment, respectively. Adalimumab concentrations in the synovial fluid from five rheumatoid arthritis patients ranged from 31 to 96% of those in serum. The pharmacokinetics of adalimumab in patients with AS were similar to those in patients with RA.

Psoriatic Arthritis: In patients receiving 40 mg every other week, adalimumab mean steady-state trough concentrations were 6 to 10 mcg/mL and 8.5 to 12 mcg/mL, without and with MTX concomitant treatment, respectively.

Plaque Psoriasis: Adalimumab mean steady-state trough concentration was approximately 5 to 6 mcg/mL during adalimumab 40 mg every other week treatment.

Adult Uveitis: Adalimumab mean steady concentration was approximately 8 to 10 mcg/mL during adalimumab 40 mg every other week treatment.

Adult Hidradenitis Suppurativa: Adalimumab trough concentrations were approximately 7 to 8 mcg/mL at Week 2 and Week 4, respectively, after receiving 160 mg on Week 0 followed by 80 mg on Week 2. Mean steady-state trough concentrations at Week 12 through Week 36 were approximately 7 to 11 mcg/mL during adalimumab 40 mg every week treatment.

Adult Crohn's Disease: Adalimumab mean trough concentrations were approximately 12 mcg/mL at Week 2 and Week 4 after receiving 160 mg on Week 0 followed by 80 mg on Week 2. Mean steady-state trough concentrations were 7 mcg/mL at Week 24 and Week 56 during adalimumab 40 mg every other week treatment.

Adult Ulcerative Colitis: Adalimumab mean trough concentrations were approximately 12 mcg/mL at Week 2 and Week 4 after receiving 160 mg on Week 0 followed by 80 mg on Week 2. Mean steady-state trough concentrations were approximately 8 mcg/mL and 15 mcg/mL at Week 52 after receiving a dose of adalimumab 40 mg every other week and 40 mg every week, respectively.

Anti-Drug Antibody Effects on Pharmacokinetics

Rheumatoid Arthritis: A trend toward higher apparent clearance of adalimumab in the presence of anti-adalimumab antibodies was identified.

Hidradenitis Suppurativa: In subjects with moderate to severe HS, antibodies to adalimumab were associated with reduced serum adalimumab concentrations. In general, the extent of reduction in serum adalimumab concentrations is greater with increasing titers of antibodies to adalimumab.

Specific Populations

Geriatric Patients: A lower clearance with increasing age was observed in patients with RA aged 40 to >75 years.

Pediatric Patients:

Juvenile Idiopathic Arthritis:

- 4 years to 17 years of age: The adalimumab mean steady-state trough concentrations were 6.8 mcg/mL and 10.9 mcg/mL in patients weighing <30 kg receiving 20 mg adalimumab subcutaneously every other week as monotherapy or with concomitant MTX, respectively. The adalimumab mean steady-state trough concentrations were 6.6 mcg/mL and 8.1 mcg/mL in patients weighing ≥30 kg receiving 40 mg adalimumab subcutaneously every other week as monotherapy or with MTX concomitant treatment, respectively.
- 2 years to <4 years of age or 4 years of age and older weighing <15 kg: The adalimumab mean steady-state trough adalimumab concentrations were 6.0 mcg/mL and 7.9 mcg/mL in patients receiving adalimumab subcutaneously every other week as monotherapy or with MTX concomitant treatment, respectively.

Pediatric Crohn's Disease: Adalimumab mean ± SD concentrations were 15.7±6.5 mcg/mL at Week 4 following 160 mg at Week 0 and 80 mg at Week 2, and 10.5±6.0 mcg/mL at Week 52 following 40 mg every other week dosing in patients weighing ≥ 40 kg. Adalimumab mean ± SD concentrations were 10.6±6.1 mcg/mL at Week 4 following dosing 80 mg at Week 0 and 40 mg at Week 2, and 6.9±3.6 mcg/mL at Week 52 following 20 mg every other week dosing in patients weighing < 40 kg.

Male and Female Patients: No gender-related pharmacokinetic differences were observed after correction for a patient's body weight. Healthy subjects and patients with rheumatoid arthritis displayed similar adalimumab pharmacokinetics.

Patients with Renal or Hepatic Impairment: No pharmacokinetic data are available in patients with hepatic or renal impairment.

Rheumatoid factor or CRP concentrations: Minor increases in apparent clearance were predicted in RA patients receiving doses lower than the recommended dose and in RA patients with high rheumatoid factor or CRP concentrations. These increases are not likely to be clinically important.

Drug Interaction Studies:

Methotrexate: MTX reduced adalimumab apparent clearance after single and multiple dosing by 29% and 44% respectively, in patients with RA [see Drug Interactions (7.1)].

13 NONCLINICAL TOXICOLOGY

13.1 Carcinogenesis, Mutagenesis, Impairment of Fertility

Long-term animal studies of adalimumab products have not been conducted to evaluate the carcinogenic potential or its effect on fertility.

14 CLINICAL STUDIES

14.1 Rheumatoid Arthritis

The efficacy and safety of adalimumab were assessed in five randomized, double-blind studies in patients ≥18 years of age with active rheumatoid arthritis (RA) diagnosed according to American College of Rheumatology (ACR) criteria. Patients had at least 6 swollen and 9 tender joints. Adalimumab was administered subcutaneously in combination with methotrexate (MTX) (12.5 to 25 mg, Studies RA-I, RA-III and RA-V) or as monotherapy (Studies RA-II and RA-V) or with other disease-modifying anti-rheumatic drugs (DMARDs) (Study RA-IV).

Study RA-I evaluated 271 patients who had failed therapy with at least one but no more than four DMARDs and had inadequate response to MTX. Doses of 20, 40 or 80 mg of adalimumab or placebo were given every other week for 24 weeks.

Study RA-II evaluated 544 patients who had failed therapy with at least one DMARD. Doses of placebo, 20 or 40 mg of adalimumab were given as monotherapy every other week or weekly for 26 weeks.

Study RA-III evaluated 619 patients who had an inadequate response to MTX. Patients received placebo, 40 mg of adalimumab every other week with placebo injections on alternate weeks, or 20 mg of adalimumab weekly for up to 52 weeks. Study RA-III had an additional primary endpoint at 52 weeks of inhibition of disease progression (as detected by X-ray results). Upon completion of the first 52 weeks, 457 patients enrolled in an open-label extension phase in which 40 mg of adalimumab was administered every other week for up to 5 years.

Study RA-IV assessed safety in 636 patients who were either DMARD-naive or were permitted to remain on their pre-existing rheumatologic therapy provided that therapy was stable for a minimum of 28 days. Patients were randomized to 40 mg of adalimumab or placebo every other week for 24 weeks.

Study RA-V evaluated 799 patients with moderately to severely active RA of less than 3 years duration who were ≥18 years old and MTX naïve. Patients were randomized to receive either MTX (optimized to 20 mg/week by week 8), adalimumab 40 mg every other week or adalimumab/MTX combination therapy for 104 weeks. Patients were evaluated for signs and symptoms, and for radiographic progression of joint damage. The median disease duration among patients enrolled in the study was 5 months. The median MTX dose achieved was 20 mg.

Clinical Response

The percent of adalimumab treated patients achieving ACR 20, 50 and 70 responses in Studies RA-II and III are shown in Table 3.

Table 3. ACR Responses in Studies RA-II and RA-III (Percent of Patients)
 | Study RA-II Monotherapy (26 weeks) |  |  | Study RA-III Methotrexate Combination (24 and 52 weeks)
Response | Placebo | Adalimumab | Adalimumab | Placebo/MTX | Adalimumab/MTX
 |  | 40 mg every | 40 mg weekly |  | 40 mg every
 |  | other week |  |  | other week
 | N=110 | N=113 | N=103 | N=200 | N=207
ACR20
Month 6 | 19% | 46%* | 53%* | 30% | 63%*
Month 12 | NA | NA | NA | 24% | 59%*
ACR50
Month 6 | 8% | 22%* | 35%* | 10% | 39%*
Month 12 | NA | NA | NA | 10% | 42%*
ACR70
Month 6 | 2% | 12%* | 18%* | 3% | 21%*
Month 12 | NA | NA | NA | 5% | 23%*
* p<0.01, adalimumab vs.placebo

The results of Study RA-I were similar to Study RA-III; patients receiving adalimumab 40 mg every other week in Study RA-I also achieved ACR 20, 50 and 70 response rates of 65%, 52% and 24%, respectively, compared to placebo responses of 13%, 7% and 3% respectively, at 6 months (p<0.01).

The results of the components of the ACR response criteria for Studies RA-II and RA-III are shown in Table 4. ACR response rates and improvement in all components of ACR response were maintained to week 104. Over the 2 years in Study RA-III, 20% of adalimumab patients receiving 40 mg every other week achieved a major clinical response, defined as maintenance of an ACR 70 response over a 6-month period. ACR responses were maintained in similar proportions of patients for up to 5 years with continuous adalimumab treatment in the open-label portion of Study RA-III.

Table 4. Components of ACR Response in Studies RA-II and RA-III
 | Study RA-II |  |  |  | Study RA-III
Parameter (median) | Placebo N=110 |  | Adalimumaba N=113 |  | Placebo/MTX N=200 |  | Adalimumaba/MTX N=207
 | Baseline | Wk 26 | Baseline | Wk 26 | Baseline | Wk 24 | Baseline | Wk 24
Number of tender joints (0-68) | 35 | 26 | 31 | 16* | 26 | 15 | 24 | 8*
Number of swollen joints (0-66) | 19 | 16 | 18 | 10* | 17 | 11 | 18 | 5*
Physician global assessmentb | 7.0 | 6.1 | 6.6 | 3.7* | 6.3 | 3.5 | 6.5 | 2.0*
Patient global assessmentb | 7.5 | 6.3 | 7.5 | 4.5* | 5.4 | 3.9 | 5.2 | 2.0*
Painb | 7.3 | 6.1 | 7.3 | 4.1* | 6.0 | 3.8 | 5.8 | 2.1*
Disability index (HAQ)c | 2.0 | 1.9 | 1.9 | 1.5* | 1.5 | 1.3 | 1.5 | 0.8*
CRP (mg/dL) | 3.9 | 4.3 | 4.6 | 1.8* | 1.0 | 0.9 | 1.0 | 0.4*
40 mg adalimumab administered every other week
b Visual analogue scale; 0 = best, 10 = worst
c Disability Index of the Health Assessment Questionnaire; 0 = best, 3 = worst, measures the patient's ability to perform the following: dress/groom, arise, eat, walk, reach, grip, maintain hygiene, and maintain daily activity
* p<0.001, adalimumab vs. placebo, based on mean change from baseline

The time course of ACR 20 response for Study RA-III is shown in Figure 1.

In Study RA-III, 85% of patients with ACR 20 responses at week 24 maintained the response at 52 weeks. The time course of ACR 20 response for Study RA-I and Study RA-II were similar.

Figure 1. Study RA-III ACR 20 Responses over 52 Weeks

In Study RA-IV, 53% of patients treated with adalimumab 40 mg every other week plus standard of care had an ACR 20 response at week 24 compared to 35% on placebo plus standard of care (p<0.001). No unique adverse reactions related to the combination of adalimumab and other DMARDs were observed.

In Study RA-V with MTX naïve patients with recent onset RA, the combination treatment with adalimumab plus MTX led to greater percentages of patients achieving ACR responses than either MTX monotherapy or adalimumab monotherapy at Week 52 and responses were sustained at Week 104 (see Table 5).

Table 5. ACR Response in Study RA-V (Percent of Patients)
Response | MTXb N=257 | Adalimumabc N=274 | Adalimumab/MTX N=268
ACR20 Week 52 Week 104 | 63% 56% | 54% 49% | 73% 69%
ACR50 Week 52 Week 104 | 46% 43% | 41% 37% | 62% 59%
ACR70 Week 52 Week 104 | 27% 28% | 26% 28% | 46% 47%
Major Clinical Response a | 28% | 25% | 49%
a Major clinical response is defined as achieving an ACR70 response for a continuous six month period
b p<0.05, adalimumab/MTX vs. MTX for ACR 20
p<0.001, adalimumab/MTX vs. MTX for ACR 50 and 70, and Major Clinical Response
c p<0.001, adalimumab/MTX vs. adalimumab

At Week 52, all individual components of the ACR response criteria for Study RA-V improved in the adalimumab/MTX group and improvements were maintained to Week 104.

Radiographic Response

In Study RA-III, structural joint damage was assessed radiographically and expressed as change in Total Sharp Score (TSS) and its components, the erosion score and Joint Space Narrowing (JSN) score, at month 12 compared to baseline. At baseline, the median TSS was approximately 55 in the placebo and 40 mg every other week groups. The results are shown in Table 6. Adalimumab/MTX treated patients demonstrated less radiographic progression than patients receiving MTX alone at 52 weeks.

Table 6. Radiographic Mean Changes Over 12 Months in Study RA-III
 | Placebo/MTX | Adalimumab/MTX 40 mg every other week | Placebo/MTX-Adalimumab/MTX (95% Confidence Interval*) | P-value**
Total Sharp score | 2.7 | 0.1 | 2.6 (1.4, 3.8) | <0.001
Erosion score | 1.6 | 0.0 | 1.6 (0.9, 2.2) | <0.001
JSN score | 1.0 | 0.1 | 0.9 (0.3, 1.4) | 0.002
*95% confidence intervals for the differences in change scores between MTX and adalimumab.
**Based on rank analysis

In the open-label extension of Study RA-III, 77% of the original patients treated with any dose of adalimumab were evaluated radiographically at 2 years. Patients maintained inhibition of structural damage, as measured by the TSS. Fifty-four percent had no progression of structural damage as defined by a change in the TSS of zero or less. Fifty-five percent (55%) of patients originally treated with 40 mg adalimumab every other week have been evaluated radiographically at 5 years. Patients had continued inhibition of structural damage with 50% showing no progression of structural damage defined by a change in the TSS of zero or less.

In Study RA-V, structural joint damage was assessed as in Study RA-III. Greater inhibition of radiographic progression, as assessed by changes in TSS, erosion score and JSN was observed in the adalimumab/MTX combination group as compared to either the MTX or adalimumab monotherapy group at Week 52 as well as at Week 104 (see Table 7).

Table 7. Radiographic Mean Change* in Study RA-V
 |  | MTXa N=257 | Adalimumaba,b N=274 | Adalimumab/MTX N=268
52 Weeks | Total Sharp score | 5.7 (4.2, 7.3) | 3.0 (1.7, 4.3) | 1.3 (0.5, 2.1)
 | Erosion score | 3.7 (2.7, 4.8) | 1.7 (1.0, 2.4) | 0.8 (0.4, 1.2)
 | JSN score | 2.0 (1.2, 2.8) | 1.3 (0.5, 2.1) | 0.5 (0.0, 1.0)
104 Weeks | Total Sharp score | 10.4 (7.7, 13.2) | 5.5 (3.6, 7.4) | 1.9 (0.9, 2.9)
 | Erosion score | 6.4 (4.6, 8.2) | 3.0 (2.0, 4.0) | 1.0 (0.4, 1.6)
 | JSN score | 4.1 (2.7, 5.4) | 2.6 (1.5, 3.7) | 0.9 (0.3, 1.5)
* mean (95% confidence interval)
a p<0.001, adalimumab /MTX vs. MTX at 52 and 104 weeks and for adalimumab /MTX vs adalimumab at 104 weeks
b p<0.01, for adalimumab /MTX vs. adalimumab at 52 weeks

Physical Function Response

In studies RA-I through IV, adalimumab showed significantly greater improvement than placebo in the disability index of Health Assessment Questionnaire (HAQ-DI) from baseline to the end of study, and significantly greater improvement than placebo in the health-outcomes as assessed by The Short Form Health Survey (SF 36). Improvement was seen in both the Physical Component Summary (PCS) and the Mental Component Summary (MCS).

In Study RA-III, the mean (95% CI) improvement in HAQ-DI from baseline at week 52 was 0.60 (0.55, 0.65) for the adalimumab patients and 0.25 (0.17, 0.33) for placebo/MTX (p<0.001) patients. Sixty-three percent of adalimumab-treated patients achieved a 0.5 or greater improvement in HAQ-DI at week 52 in the double-blind portion of the study. Eighty-two percent of these patients maintained that improvement through week 104 and a similar proportion of patients maintained this response through week 260 (5 years) of open-label treatment. Mean improvement in the SF-36 was maintained through the end of measurement at week 156 (3 years).

In Study RA-V, the HAQ-DI and the physical component of the SF-36 showed greater improvement (p<0.001) for the adalimumab/MTX combination therapy group versus either the MTX monotherapy or the adalimumab monotherapy group at Week 52, which was maintained through Week 104.

14.2 Juvenile Idiopathic Arthritis

The safety and efficacy of adalimumab was assessed in two studies (Studies JIA-I and JIA-II) in patients with active polyarticular juvenile idiopathic arthritis (JIA).

Study JIA-I

The safety and efficacy of adalimumab were assessed in a multicenter, randomized, withdrawal, double-blind, parallel-group study in 171 patients who were 4 to 17 years of age with polyarticular JIA. In the study, the patients were stratified into two groups: MTX-treated or non-MTX-treated. All patients had to show signs of active moderate or severe disease despite previous treatment with NSAIDs, analgesics, corticosteroids, or DMARDS. Patients who received prior treatment with any biologic DMARDS were excluded from the study.

The study included four phases: an open-label lead in phase (OL-LI; 16 weeks), a double-blind randomized withdrawal phase (DB; 32 weeks), an open-label extension phase (OLE-BSA; up to 136 weeks), and an open-label fixed dose phase (OLE-FD; 16 weeks). In the first three phases of the study, adalimumab was administered based on body surface area at a dose of 24 mg/m^2 up to a maximum total body dose of 40 mg subcutaneously (SC) every other week. In the OLE-FD phase, the patients were treated with 20 mg of adalimumab SC every other week if their weight was less than 30 kg and with 40 mg of adalimumab SC every other week if their weight was 30 kg or greater. Patients remained on stable doses of NSAIDs and or prednisone (≤0.2 mg/kg/day or 10 mg/day maximum).

Patients demonstrating a Pediatric ACR 30 response at the end of OL-LI phase were randomized into the double blind (DB) phase of the study and received either adalimumab or placebo every other week for 32 weeks or until disease flare. Disease flare was defined as a worsening of ≥30% from baseline in ≥3 of 6 Pediatric ACR core criteria, ≥2 active joints, and improvement of >30% in no more than 1 of the 6 criteria. After 32 weeks or at the time of disease flare during the DB phase, patients were treated in the open-label extension phase based on the BSA regimen (OLE- BSA), before converting to a fixed dose regimen based on body weight (OLE-FD phase).

Study JIA-I Clinical Response

At the end of the 16-week OL-LI phase, 94% of the patients in the MTX stratum and 74% of the patients in the non-MTX stratum were Pediatric ACR 30 responders. In the DB phase significantly fewer patients who received adalimumab experienced disease flare compared to placebo, both without MTX (43% vs. 71%) and with MTX (37% vs. 65%). More patients treated with adalimumab continued to show pediatric ACR 30/50/70 responses at Week 48 compared to patients treated with placebo. Pediatric ACR responses were maintained for up to two years in the OLE phase in patients who received adalimumab throughout the study.

Study JIA-II

Adalimumab was assessed in an open-label, multicenter study in 32 patients who were 2 to <4 years of age or 4 years of age and older weighing <15 kg with moderately to severely active polyarticular JIA. Most patients (97%) received at least 24 weeks of adalimumab treatment dosed 24 mg/m^2 up to a maximum of 20 mg every other week as a single SC injection up to a maximum of 120 weeks duration. During the study, most patients used concomitant MTX, with fewer reporting use of corticosteroids or NSAIDs. The primary objective of the study was evaluation of safety [see Adverse Reactions (6.1)].

14.3 Psoriatic Arthritis

The safety and efficacy of adalimumab was assessed in two randomized, double-blind, placebo controlled studies in 413 patients with psoriatic arthritis (PsA). Upon completion of both studies, 383 patients enrolled in an open-label extension study, in which 40 mg adalimumab was administered every other week.

Study PsA-I enrolled 313 adult patients with moderately to severely active PsA (>3 swollen and >3 tender joints) who had an inadequate response to NSAID therapy in one of the following forms: (1) distal interphalangeal (DIP) involvement (N=23); (2) polyarticular arthritis (absence of rheumatoid nodules and presence of plaque psoriasis) (N=210); (3) arthritis mutilans (N=1); (4) asymmetric PsA (N=77); or (5) AS-like (N=2). Patients on MTX therapy (158 of 313 patients) at enrollment (stable dose of ≤30 mg/week for >1 month) could continue MTX at the same dose. Doses of adalimumab 40 mg or placebo every other week were administered during the 24-week double-blind period of the study.

Compared to placebo, treatment with adalimumab resulted in improvements in the measures of disease activity (see Tables 8 and 9). Among patients with PsA who received adalimumab, the clinical responses were apparent in some patients at the time of the first visit (two weeks) and were maintained up to 88 weeks in the ongoing open-label study. Similar responses were seen in patients with each of the subtypes of psoriatic arthritis, although few patients were enrolled with the arthritis mutilans and ankylosing spondylitis-like subtypes. Responses were similar in patients who were or were not receiving concomitant MTX therapy at baseline.

Patients with psoriatic involvement of at least three percent body surface area (BSA) were evaluated for Psoriatic Area and Severity Index (PASI) responses. At 24 weeks, the proportions of patients achieving a 75% or 90% improvement in the PASI were 59% and 42% respectively, in the adalimumab group (N=69), compared to 1% and 0% respectively, in the placebo group (N=69) (p<0.001). PASI responses were apparent in some patients at the time of the first visit (two weeks). Responses were similar in patients who were or were not receiving concomitant MTX therapy at baseline.

Table 8. ACR Response in Study PsA-I (Percent of Patients)
 | Placebo N=162 | Adalimumab* N=151
ACR20 Week 12 Week 24 | 14% 15% | 58% 57%
ACR50 Week 12 Week 24 | 4% 6% | 36% 39%
ACR70 Week 12 Week 24 | 1% 1% | 20% 23%
* p<0.001 for all comparisons between adalimumab and placebo

Table 9. Components of Disease Activity in Study PsA-I
 | Placebo N=162 |  | Adalimumab* N=151
Parameter: median | Baseline | 24 weeks | Baseline | 24 weeks
Number of tender jointsa | 23.0 | 17.0 | 20.0 | 5.0
Number of swollen jointsb | 11.0 | 9.0 | 11.0 | 3.0
Physician global assessmentc | 53.0 | 49.0 | 55.0 | 16.0
Patient global assessmentc | 49.5 | 49.0 | 48.0 | 20.0
Painc | 49.0 | 49.0 | 54.0 | 20.0
Disability index (HAQ) d | 1.0 | 0.9 | 1.0 | 0.4
CRP (mg/dL)e | 0.8 | 0.7 | 0.8 | 0.2
* p<0.001 for adalimumab vs. placebo comparisons based on median changes
a Scale 0-78
b Scale 0-76
c Visual analog scale; 0=best, 100=worst
d Disability Index of the Health Assessment Questionnaire; 0=best, 3=worst; measures the patient's ability to perform the following: dress/groom, arise, eat, walk, reach, grip, maintain hygiene, and maintain daily activity.
e Normal range: 0-0.287 mg/dL

Similar results were seen in an additional, 12-week study in 100 patients with moderate to severe psoriatic arthritis who had suboptimal response to DMARD therapy as manifested by ≥3 tender joints and ≥3 swollen joints at enrollment.

Radiographic Response

Radiographic changes were assessed in the PsA studies. Radiographs of hands, wrists, and feet were obtained at baseline and Week 24 during the double-blind period when patients were on adalimumab or placebo and at Week 48 when all patients were on open-label adalimumab. A modified Total Sharp Score (mTSS), which included distal interphalangeal joints (i.e., not identical to the TSS used for rheumatoid arthritis), was used by readers blinded to treatment group to assess the radiographs.

Adalimumab-treated patients demonstrated greater inhibition of radiographic progression compared to placebo-treated patients and this effect was maintained at 48 weeks (see Table 10).

Table 10. Change in Modified Total Sharp Score in Psoriatic Arthritis
 | Placebo N=141 | Adalimumab N=133
 | Week 24 | Week 24 | Week 48
Baseline mean | 22.1 | 23.4 | 23.4
Mean Change ± SD | 0.9 ± 3.1 | -0.1 ± 1.7 | -0.2 ± 4.9*
* <0.001 for the difference between adalimumab, Week 48 and Placebo, Week 24 (primary analysis)

Physical Function Response

In Study PsA-I, physical function and disability were assessed using the HAQ Disability Index (HAQ-DI) and the SF-36 Health Survey. Patients treated with 40 mg of adalimumab every other week showed greater improvement from baseline in the HAQ-DI score (mean decreases of 47% and 49% at Weeks 12 and 24 respectively) in comparison to placebo (mean decreases of 1% and 3% at Weeks 12 and 24 respectively). At Weeks 12 and 24, patients treated with adalimumab showed greater improvement from baseline in the SF-36 Physical Component Summary score compared to patients treated with placebo, and no worsening in the SF-36 Mental Component Summary score. Improvement in physical function based on the HAQ-DI was maintained for up to 84 weeks through the open-label portion of the study.

14.4 Ankylosing Spondylitis

The safety and efficacy of adalimumab 40 mg every other week was assessed in 315 adult patients in a randomized, 24 week double-blind, placebo-controlled study in patients with active ankylosing spondylitis (AS) who had an inadequate response to glucocorticoids, NSAIDs, analgesics, methotrexate or sulfasalazine. Active AS was defined as patients who fulfilled at least two of the following three criteria: (1) a Bath AS disease activity index (BASDAI) score ≥4 cm, (2) a visual analog score (VAS) for total back pain ≥ 40 mm, and (3) morning stiffness ≥ 1 hour. The blinded period was followed by an open-label period during which patients received adalimumab 40 mg every other week subcutaneously for up to an additional 28 weeks.

Improvement in measures of disease activity was first observed at Week 2 and maintained through 24 weeks as shown in Figure 2 and Table 11.

Responses of patients with total spinal ankylosis (n=11) were similar to those without total ankylosis.

Figure 2. ASAS 20 Response By Visit, Study AS-I

At 12 weeks, the ASAS 20/50/70 responses were achieved by 58%, 38%, and 23%, respectively, of patients receiving adalimumab, compared to 21%, 10%, and 5% respectively, of patients receiving placebo (p <0.001). Similar responses were seen at Week 24 and were sustained in patients receiving open-label adalimumab for up to 52 weeks.

A greater proportion of patients treated with adalimumab (22%) achieved a low level of disease activity at 24 weeks (defined as a value <20 [on a scale of 0 to 100 mm] in each of the four ASAS response parameters) compared to patients treated with placebo (6%).

Table 11. Components of Ankylosing Spondylitis Disease Activity
 | Placebo N=107 |  | Adalimumab N=208
 | Baseline mean | Week 24 mean | Baseline mean | Week 24 mean
ASAS 20 Response Criteria*
Patient's Global Assessment of Disease Activitya* | 65 | 60 | 63 | 38
Total back pain* | 67 | 58 | 65 | 37
Inflammationb* | 6.7 | 5.6 | 6.7 | 3.6
BASFIc* | 56 | 51 | 52 | 34
BASDAId score* | 6.3 | 5.5 | 6.3 | 3.7
BASMIe score* | 4.2 | 4.1 | 3.8 | 3.3
Tragus to wall (cm) | 15.9 | 15.8 | 15.8 | 15.4
Lumbar flexion (cm) | 4.1 | 4.0 | 4.2 | 4.4
Cervical rotation (degrees) | 42.2 | 42.1 | 48.4 | 51.6
Lumbar side flexion (cm) | 8.9 | 9.0 | 9.7 | 11.7
Intermalleolar distance (cm) | 92.9 | 94.0 | 93.5 | 100.8
CRPf* | 2.2 | 2.0 | 1.8 | 0.6
a Percent of subjects with at least a 20% and 10-unit improvement measured on a Visual Analog Scale (VAS) with 0 = “none” and 100 = “severe”
b mean of questions 5 and 6 of BASDAI (defined in ‘d’)
c Bath Ankylosing Spondylitis Functional Index
d Bath Ankylosing Spondylitis Disease Activity Index
e Bath Ankylosing Spondylitis Metrology Index
f C-Reactive Protein (mg/dL)
* statistically significant for comparisons between adalimumab and placebo at Week 24

A second randomized, multicenter, double-blind, placebo-controlled study of 82 patients with ankylosing spondylitis showed similar results.

Patients treated with adalimumab achieved improvement from baseline in the Ankylosing Spondylitis Quality of Life Questionnaire (ASQoL) score (-3.6 vs. -1.1) and in the Short Form Health Survey (SF-36) Physical Component Summary (PCS) score (7.4 vs. 1.9) compared to placebo-treated patients at Week 24.

14.5 Adult Crohn's Disease

The safety and efficacy of multiple doses of adalimumab were assessed in adult patients with moderately to severely active Crohn's disease, CD, (Crohn's Disease Activity Index (CDAI) ≥ 220 and ≤ 450) in randomized, double-blind, placebo-controlled studies. Concomitant stable doses of aminosalicylates, corticosteroids, and/or immunomodulatory agents were permitted, and 79% of patients continued to receive at least one of these medications.

Induction of clinical remission (defined as CDAI < 150) was evaluated in two studies. In Study CD-I, 299 TNF-blocker naïve patients were randomized to one of four treatment groups: the placebo group received placebo at Weeks 0 and 2, the 160/80 group received 160 mg adalimumab at Week 0 and 80 mg at Week 2, the 80/40 group received 80 mg at Week 0 and 40 mg at Week 2, and the 40/20 group received 40 mg at Week 0 and 20 mg at Week 2. Clinical results were assessed at Week 4.

In the second induction study, Study CD-II, 325 patients who had lost response to, or were intolerant to, previous infliximab therapy were randomized to receive either 160 mg adalimumab at Week 0 and 80 mg at Week 2, or placebo at Weeks 0 and 2. Clinical results were assessed at Week 4.

Maintenance of clinical remission was evaluated in Study CD-III. In this study, 854 patients with active disease received open-label adalimumab, 80 mg at week 0 and 40 mg at Week 2. Patients were then randomized at Week 4 to 40 mg adalimumab every other week, 40 mg adalimumab every week, or placebo. The total study duration was 56 weeks. Patients in clinical response (decrease in CDAI ≥70) at Week 4 were stratified and analyzed separately from those not in clinical response at Week 4.

Induction of Clinical Remission

A greater percentage of the patients treated with 160/80 mg adalimumab achieved induction of clinical remission versus placebo at Week 4 regardless of whether the patients were TNF blocker naïve (CD-I), or had lost response to or were intolerant to infliximab (CD-II) (see Table 12).

Table 12. Induction of Clinical Remission in Studies CD-I and CD-II (Percent of Patients)
 | CD-I |  | CD-II
 | Placebo N=74 | Adalimumab 160/80 mg N=76 | Placebo N=166 | Adalimumab 160/80 mg N=159
Week 4
Clinical remission | 12% | 36%* | 7% | 21%*
Clinical response | 34% | 58%** | 34% | 52%**
Clinical remission is CDAI score < 150; clinical response is decrease in CDAI of at least 70 points.
* p<0.001 for adalimumab vs. placebo pairwise comparison of proportions
** p<0.01 for adalimumab vs. placebo pairwise comparison of proportions

Maintenance of Clinical Remission

In Study CD-III at Week 4, 58% (499/854) of patients were in clinical response and were assessed in the primary analysis. At Weeks 26 and 56, greater proportions of patients who were in clinical response at Week 4 achieved clinical remission in the adalimumab 40 mg every other week maintenance group compared to patients in the placebo maintenance group (see Table 13). The group that received adalimumab therapy every week did not demonstrate significantly higher remission rates compared to the group that received adalimumab every other week.

Table 13. Maintenance of Clinical Remission in CD-III (Percent of Patients)
 | Placebo | 40 mg Adalimumab every other week
 | N=170 | N=172
Week 26
Clinical remission | 17% | 40%*
Clinical response | 28% | 54%*
Week 56
Clinical remission | 12% | 36%*
Clinical response | 18% | 43%*
Clinical remission is CDAI score < 150; clinical response is decrease in CDAI of at least 70 points.
*p<0.001 for adalimumab vs. placebo pairwise comparisons of proportions

Of those in response at Week 4 who attained remission during the study, patients in the adalimumab every other week group maintained remission for a longer time than patients in the placebo maintenance group. Among patients who were not in response by Week 12, therapy continued beyond 12 weeks did not result in significantly more responses.

14.6 Pediatric Crohn's Disease

A randomized, double-blind, 52-week clinical study of 2 dose concentrations of adalimumab (Study PCD-I) was conducted in 192 pediatric patients (6 to 17 years of age) with moderately to severely active Crohn's disease (defined as Pediatric Crohn's Disease Activity Index (PCDAI) score > 30). Enrolled patients had over the previous two year period an inadequate response to corticosteroids or an immunomodulator (i.e., azathioprine, 6-mercaptopurine, or methotrexate). Patients who had previously received a TNF blocker were allowed to enroll if they had previously had loss of response or intolerance to that TNF blocker.

Patients received open-label induction therapy at a dose based on their body weight (≥40 kg and <40 kg). Patients weighing ≥40 kg received 160 mg (at Week 0) and 80 mg (at Week 2). Patients weighing <40 kg received 80 mg (at Week 0) and 40 mg (at Week 2). At Week 4, patients within each body weight category (≥40 kg and <40 kg) were randomized 1:1 to one of two maintenance dose regimens (high dose and low dose). The high dose was 40 mg every other week for patients weighing ≥40 kg and 20 mg every other week for patients weighing <40 kg. The low dose was 20 mg every other week for patients weighing ≥40 kg and 10 mg every other week for patients weighing <40 kg.

Concomitant stable dosages of corticosteroids (prednisone dosage ≤40 mg/day or equivalent) and immunomodulators (azathioprine, 6-mercaptopurine, or methotrexate) were permitted throughout the study.

At Week 12, patients who experienced a disease flare (increase in PCDAI of ≥ 15 from Week 4 and absolute PCDAI > 30) or who were non-responders (did not achieve a decrease in the PCDAI of ≥ 15 from baseline for 2 consecutive visits at least 2 weeks apart) were allowed to dose-escalate (i.e., switch from blinded every other week dosing to blinded every week dosing); patients who dose-escalated were considered treatment failures.

At baseline, 38% of patients were receiving corticosteroids, and 62% of patients were receiving an immunomodulator. Forty-four percent (44%) of patients had previously lost response or were intolerant to a TNF blocker. The median baseline PCDAI score was 40.

Of the 192 patients total, 188 patients completed the 4 week induction period, 152 patients completed 26 weeks of treatment, and 124 patients completed 52 weeks of treatment. Fifty-one percent (51%) (48/95) of patients in the low maintenance dose group dose-escalated, and 38% (35/93) of patients in the high maintenance dose group dose-escalated.

At Week 4, 28% (52/188) of patients were in clinical remission (defined as PCDAI ≤ 10).

The proportions of patients in clinical remission (defined as PCDAI ≤ 10) and clinical response (defined as reduction in PCDAI of at least 15 points from baseline) were assessed at Weeks 26 and 52.

At both Weeks 26 and 52, the proportion of patients in clinical remission and clinical response was numerically higher in the high dose group compared to the low dose group (Table 14). The recommended maintenance regimen is 20 mg every other week for patients weighing < 40 kg and 40 mg every other week for patients weighing ≥ 40 kg. Every week dosing is not the recommended maintenance dosing regimen [see Dosage and Administration (2.3)].

Table 14. Clinical Remission and Clinical Response in Study PCD-I
 | Low Maintenance Dose† (20 or 10 mg every other week) N = 95 | High Maintenance Dose# (40 or 20 mg every other week) N = 93
Week 26
Clinical Remission‡ | 28% | 39%
Clinical Response§ | 48% | 59%
Week 52
Clinical Remission‡ | 23% | 33%
Clinical Response§ | 28% | 42%
†The low maintenance dose was 20 mg every other week for patients weighing ≥ 40 kg and 10
mg every other week for patients weighing < 40 kg.
#The high maintenance dose was 40 mg every other week for patients weighing ≥ 40 kg and 20
mg every other week for patients weighing < 40 kg.
‡Clinical remission defined as PCDAI ≤ 10.
§Clinical response defined as reduction in PCDAI of at least 15 points from baseline.

14.7 Adult Ulcerative Colitis

The safety and efficacy of adalimumab were assessed in adult patients with moderately to severely active ulcerative colitis (Mayo score 6 to 12 on a 12 point scale, with an endoscopy subscore of 2 to 3 on a scale of 0 to 3) despite concurrent or prior treatment with immunosuppressants such as corticosteroids, azathioprine, or 6-MP in two randomized, double-blind, placebo-controlled clinical studies (Studies UC-I and UC-II). Both studies enrolled TNF-blocker naïve patients, but Study UC-II also allowed entry of patients who lost response to or were intolerant to TNF- blockers. Forty percent (40%) of patients enrolled in Study UC-II had previously used another TNF-blocker.

Concomitant stable doses of aminosalicylates and immunosuppressants were permitted. In Studies UC-I and II, patients were receiving aminosalicylates (69%), corticosteroids (59%) and/or azathioprine or 6-MP (37%) at baseline. In both studies, 92% of patients received at least one of these medications.

Induction of clinical remission (defined as Mayo score ≤ 2 with no individual subscores > 1) at Week 8 was evaluated in both studies. Clinical remission at Week 52 and sustained clinical remission (defined as clinical remission at both Weeks 8 and 52) were evaluated in Study UC-II.

In Study UC-I, 390 TNF-blocker naïve patients were randomized to one of three treatment groups for the primary efficacy analysis. The placebo group received placebo at Weeks 0, 2, 4 and 6. The 160/80 group received 160 mg adalimumab at Week 0 and 80 mg at Week 2, and the 80/40 group received 80 mg adalimumab at Week 0 and 40 mg at Week 2. After Week 2, patients in both adalimumab treatment groups received 40 mg every other week.

In Study UC-II, 518 patients were randomized to receive either adalimumab 160 mg at Week 0, 80 mg at Week 2, and 40 mg every other week starting at Week 4 through Week 50, or placebo starting at Week 0 and every other week through Week 50. Corticosteroid taper was permitted starting at Week 8.

In both Studies UC-I and UC-II, a greater percentage of the patients treated with 160/80 mg of adalimumab compared to patients treated with placebo achieved induction of clinical remission. In Study UC-II, a greater percentage of the patients treated with 160/80 mg of adalimumab compared to patients treated with placebo achieved sustained clinical remission (clinical remission at both Weeks 8 and 52) (Table 15).

Table 15. Induction of Clinical Remission in Studies UC-I and UC-II and Sustained Clinical Remission in Study UC-II (Percent of Patients)
 | Study UC-I |  |  | Study UC-II
 | Placebo N=130 | Adalimumab 160/80 mg N=130 | Treatment Difference (95% CI) | Placebo N=246 | Adalimumab 160/80 mg N=248 | Treatment Difference (95% CI)
Induction of Clinical | 9.2% | 18.5% | 9.3%* | 9.3% | 16.5% | 7.2%*
Remission (Clinical | 9.2% | 18.5% | (0.9%, | 9.3% | 16.5% | (1.2%,
Remission at Week 8) | 9.2% | 18.5% | 17.6%) | 9.3% | 16.5% | 12.9%)
Sustained Clinical Remission (Clinical Remission at both Weeks 8 and 52) | N/A | N/A | N/A | 4.1% | 8.5% | 4.4%* (0.1%, 8.6%)
Clinical remission is defined as Mayo score ≤ 2 with no individual subscores > 1.
CI=Confidence interval
* p<0.05 for adalimumab vs. placebo pairwise comparison of proportions

In Study UC-I, there was no statistically significant difference in clinical remission observed between the adalimumab 80/40 mg group and the placebo group at Week 8.

In Study UC-II, 17.3% (43/248) in the adalimumab group were in clinical remission at Week 52 compared to 8.5% (21/246) in the placebo group (treatment difference: 8.8%; 95% confidence interval (CI): [2.8%, 14.5%]; p<0.05).

In the subgroup of patients in Study UC-II with prior TNF-blocker use, the treatment difference for induction of clinical remission appeared to be lower than that seen in the whole study population, and the treatment differences for sustained clinical remission and clinical remission at Week 52 appeared to be similar to those seen in the whole study population. The subgroup of patients with prior TNF-blocker use achieved induction of clinical remission at 9% (9/98) in the adalimumab group versus 7% (7/101) in the placebo group, and sustained clinical remission at 5% (5/98) in the adalimumab group versus 1% (1/101) in the placebo group. In the subgroup of patients with prior TNF-blocker use, 10% (10/98) were in clinical remission at Week 52 in the adalimumab group versus 3% (3/101) in the placebo group.

14.8 Plaque Psoriasis

The safety and efficacy of adalimumab were assessed in randomized, double-blind, placebo- controlled studies in 1696 adult subjects with moderate to severe chronic plaque psoriasis (Ps) who were candidates for systemic therapy or phototherapy.

Study Ps-I evaluated 1212 subjects with chronic Ps with ≥10% body surface area (BSA) involvement, Physician's Global Assessment (PGA) of at least moderate disease severity, and Psoriasis Area and Severity Index (PASI) ≥12 within three treatment periods. In period A, subjects received placebo or adalimumab at an initial dose of 80 mg at Week 0 followed by a dose of 40 mg every other week starting at Week 1. After 16 weeks of therapy, subjects who achieved at least a PASI 75 response at Week 16, defined as a PASI score improvement of at least 75% relative to baseline, entered period B and received open-label 40 mg adalimumab every other week.

After 17 weeks of open label therapy, subjects who maintained at least a PASI 75 response at Week 33 and were originally randomized to active therapy in period A were re-randomized in period C to receive 40 mg adalimumab every other week or placebo for an additional 19 weeks. Across all treatment groups the mean baseline PASI score was 19 and the baseline Physician's Global Assessment score ranged from “moderate” (53%) to “severe” (41%) to “very severe” (6%).

Study Ps-II evaluated 99 subjects randomized to adalimumab and 48 subjects randomized to placebo with chronic plaque psoriasis with ≥10% BSA involvement and PASI ≥12. Subjects received placebo, or an initial dose of 80 mg adalimumab at Week 0 followed by 40 mg every other week starting at Week 1 for 16 weeks. Across all treatment groups the mean baseline PASI score was 21 and the baseline PGA score ranged from “moderate” (41%) to “severe” (51%) to “very severe” (8%).

Studies Ps-I and II evaluated the proportion of subjects who achieved “clear” or “minimal” disease on the 6-point PGA scale and the proportion of subjects who achieved a reduction in PASI score of at least 75% (PASI 75) from baseline at Week 16 (see Table 16 and 17).

Additionally, Study Ps-I evaluated the proportion of subjects who maintained a PGA of “clear” or “minimal” disease or a PASI 75 response after Week 33 and on or before Week 52.

Table 16. Efficacy Results at 16 Weeks in Study Ps-I Number of Subjects (%)
 | Adalimumab 40 mg every other week | Placebo
 | N = 814 | N = 398
PGA: Clear or minimal* | 506 (62%) | 17 (4%)
PASI 75 | 578 (71%) | 26 (7%)
* Clear = no plaque elevation, no scale, plus or minus hyperpigmentation or diffuse pink or red coloration
Minimal = possible but difficult to ascertain whether there is slight elevation of plaque above normal skin, plus or minus surface dryness with some white coloration, plus or minus up to red coloration

Table 17. Efficacy Results at 16 Weeks in Study Ps-II Number of Subjects (%)
 | Adalimumab 40 mg every other week | Placebo
 | N = 99 | N = 48
PGA: Clear or minimal* | 70 (71%) | 5 (10%)
PASI 75 | 77 (78%) | 9 (19%)
* Clear = no plaque elevation, no scale, plus or minus hyperpigmentation or diffuse pink or red coloration
Minimal = possible but difficult to ascertain whether there is slight elevation of plaque above normal skin, plus or minus surface dryness with some white coloration, plus or minus up to red coloration

Additionally, in Study Ps-I, subjects on adalimumab who maintained a PASI 75 were re- randomized to adalimumab (N = 250) or placebo (N = 240) at Week 33. After 52 weeks of treatment with adalimumab, more subjects on adalimumab maintained efficacy when compared to subjects who were re-randomized to placebo based on maintenance of PGA of “clear” or “minimal” disease (68% vs. 28%) or a PASI 75 (79% vs. 43%).

A total of 347 stable responders participated in a withdrawal and retreatment evaluation in an open-label extension study. Median time to relapse (decline to PGA “moderate” or worse) was approximately 5 months. During the withdrawal period, no subject experienced transformation to either pustular or erythrodermic psoriasis. A total of 178 subjects who relapsed re-initiated treatment with 80 mg of adalimumab, then 40 mg every other week beginning at week 1. At week 16, 69% (123/178) of subjects had a response of PGA “clear” or “minimal”.

A randomized, double-blind study (Study Ps-III) compared the efficacy and safety of adalimumab versus placebo in 217 adult subjects. Subjects in the study had to have chronic plaque psoriasis of at least moderate severity on the PGA scale, fingernail involvement of at least moderate severity on a 5-point Physician's Global Assessment of Fingernail Psoriasis (PGA-F) scale, a Modified Nail Psoriasis Severity Index (mNAPSI) score for the target-fingernail of ≥ 8, and either a BSA involvement of at least 10% or a BSA involvement of at least 5% with a total mNAPSI score for all fingernails of ≥ 20. Subjects received an initial dose of 80 mg adalimumab followed by 40 mg every other week (starting one week after the initial dose) or placebo for 26 weeks followed by open-label adalimumab treatment for an additional 26 weeks. This study evaluated the proportion of subjects who achieved “clear” or “minimal” assessment with at least a 2-grade improvement on the PGA-F scale and the proportion of subjects who achieved at least a 75% improvement from baseline in the mNAPSI score (mNAPSI 75) at Week 26.

At Week 26, a higher proportion of subjects in the adalimumab group than in the placebo group achieved the PGA-F endpoint. Furthermore, a higher proportion of subjects in the adalimumab group than in the placebo group achieved mNAPSI 75 at Week 26 (see Table 18).

Table 18. Efficacy Results at 26 Weeks
Endpoint | Adalimumab 40 mg every other week* N=109 | Placebo N=108
PGA-F: ≥2-grade improvement and clear or minimal | 49% | 7%
mNAPSI 75 | 47% | 3%
*Subjects received 80 mg of adalimumab at Week 0, followed by 40 mg every other week starting at Week 1.

Nail pain was also evaluated and improvement in nail pain was observed in Study Ps-III.

14.9 Hidradenitis Suppurativa

Two randomized, double-blind, placebo-controlled studies (Studies HS-I and II) evaluated the safety and efficacy of adalimumab in a total of 633 adult subjects with moderate to severe hidradenitis suppurativa (HS) with Hurley Stage II or III disease and with at least 3 abscesses or inflammatory nodules. In both studies, subjects received placebo or adalimumab at an initial dose of 160 mg at Week 0, 80 mg at Week 2, and 40 mg every week starting at Week 4 and continued through Week 11. Subjects used topical antiseptic wash daily. Concomitant oral antibiotic use was allowed in Study HS-II.

Both studies evaluated Hidradenitis Suppurativa Clinical Response (HiSCR) at Week 12. HiSCR was defined as at least a 50% reduction in total abscess and inflammatory nodule count with no increase in abscess count and no increase in draining fistula count relative to baseline (see Table 18). Reduction in HS-related skin pain was assessed using a Numeric Rating Scale in patients who entered the study with an initial baseline score of 3 or greater on a 11 point scale.

In both studies, a higher proportion of adalimumab- than placebo-treated subjects achieved HiSCR (see Table 19).

Table 19. Efficacy Results at 12 Weeks in Subjects with Moderate to Severe Hidradenitis Suppurativa
 | HS Study I |  | HS Study II*
 | Placebo | Adalimumab 40 mg Weekly | Placebo | Adalimumab 40 mg Weekly
Hidradenitis Suppurativa Clinical Response (HiSCR) | N = 154 40 (26%) | N = 153 64 (42%) | N=163 45 (28%) | N=163 96 (59%)
*19.3% of subjects in Study HS-II continued baseline oral antibiotic therapy during the study.

In both studies, from Week 12 to Week 35 (Period B), subjects who had received adalimumab were re-randomized to 1 of 3 treatment groups (adalimumab 40 mg every week, adalimumab 40 mg every other week, or placebo). Subjects who had been randomized to placebo were assigned to receive adalimumab 40 mg every week (Study HS-I) or placebo (Study HS-II).

During Period B, flare of HS, defined as ≥25% increase from baseline in abscesses and inflammatory nodule counts and with a minimum of 2 additional lesions, was documented in 22 (22%) of the 100 subjects who were withdrawn from adalimumab treatment following the primary efficacy timepoint in two studies.

14.10 Adult Uveitis

The safety and efficacy of adalimumab were assessed in adult patients with non-infectious intermediate, posterior and panuveitis excluding patients with isolated anterior uveitis, in two randomized, double-masked, placebo-controlled studies (UV I and II). Patients received placebo or adalimumab at an initial dose of 80 mg followed by 40 mg every other week starting one week after the initial dose. The primary efficacy endpoint in both studies was ′time to treatment failure′.

Treatment failure was a multi-component outcome defined as the development of new inflammatory chorioretinal and/or inflammatory retinal vascular lesions, an increase in anterior chamber (AC) cell grade or vitreous haze (VH) grade or a decrease in best corrected visual acuity (BCVA).

Study UV I evaluated 217 patients with active uveitis while being treated with corticosteroids (oral prednisone at a dose of 10 to 60 mg/day). All patients received a standardized dose of prednisone 60 mg/day at study entry followed by a mandatory taper schedule, with complete corticosteroid discontinuation by Week 15.

Study UV II evaluated 226 patients with inactive uveitis while being treated with corticosteroids (oral prednisone 10 to 35 mg/day) at baseline to control their disease. Patients subsequently underwent a mandatory taper schedule, with complete corticosteroid discontinuation by Week 19.

Clinical Response

Results from both studies demonstrated statistically significant reduction of the risk of treatment failure in patients treated with adalimumab versus patients receiving placebo. In both studies, all components of the primary endpoint contributed cumulatively to the overall difference between adalimumab and placebo groups (Table 20).

Table 20. Time to Treatment Failure in Studies UV I and UV II
 | UV I |  |  | UV II
 | Placebo (N = 107) | ADALIMUMAB (N = 110) | HR [95% CI]a | Placebo (N = 111) | ADALIMUMAB (N = 115) | HR [95% CI]a
Failureb n (%) | 84 (78.5) | 60 (54.5) | 0.50 [0.36, 0.70] | 61 (55.0) | 45 (39.1) | 0.57 [0.39, 0.84]
Median Time to Failure (Months) [95% CI] | 3.0 [2.7, 3.7] | 5.6 [3.9, 9.2] | N/A | 8.3 [4.8, 12.0] | NEc | N/A
ª HR of adalimumab versus placebo from proportional hazards regression with treatment as factor.
b Treatment failure at or after Week 6 in Study UV I, or at or after Week 2 in Study UV II, was counted as event. Subjects who discontinued the study were censored at the time of dropping out.
c NE = not estimable. Fewer than half of at-risk subjects had an event.

Figure 3: Kaplan-Meier Curves Summarizing Time to Treatment Failure on or after Week 6 (Study UV I) or Week 2 (Study UV II)

Study UV I

Study UV II

Note: P# = Placebo (Number of Events/Number at Risk); A# = adalimumab (Number of Events/Number at Risk).

15 REFERENCES

1. National Cancer Institute. Surveillance, Epidemiology, and End Results Database (SEER) Program. SEER Incidence Crude Rates, 17 Registries, 2000-2007.

16 HOW SUPPLIED/STORAGE AND HANDLING

IDACIO (adalimumab-aacf) injection is supplied as a preservative-free, sterile, clear and colorless to pale yellow solution for subcutaneous administration. The following packaging configurations are available.

- IDACIO Pen Carton - 40 mg/0.8 mL (2 count)
  IDACIO is supplied in a carton containing 2 alcohol preps and one tray. The tray contains two single-dose pens, each containing a 1 mL prefilled glass syringe with a 29 gauge staked ½ inch needle, providing 40 mg/0.8 mL of IDACIO. The syringe plunger stopper and needle cover are not made with natural rubber latex. The NDC number is 65219-554-08
- IDACIO Pen 40 mg/0.8 mL - Starter Package for Plaque Psoriasis or Uveitis (4 Count)
  IDACIO is supplied in a carton containing 4 alcohol preps and 2 trays (Starter Package for Plaque Psoriasis or Uveitis). Each tray contains two single-dose pens, each pen containing a 1 mL prefilled glass syringe with a 29 gauge staked ½ inch needle, providing 40 mg/0.8 mL of IDACIO. The syringe plunger stopper and needle cover are not made with natural rubber latex. The NDC number is 65219-554-28.
- IDACIO Pen 40 mg/0.8 mL - Starter Package for Crohn's Disease, Ulcerative Colitis, or Hidradenitis Suppurativa (6 Count)
  IDACIO is supplied in a carton containing 6 alcohol preps and 3 trays (Starter Package for Crohn's Disease, Ulcerative Colitis, or Hidradenitis Suppurativa). Each tray contains two single-dose pens, each pen containing a 1 mL prefilled glass syringe with a 29 gauge staked ½ inch needle, providing 40 mg/0.8 mL of IDACIO. The syringe plunger stopper and needle cover are not made with natural rubber latex.
  The NDC number is 65219-554-38.
- IDACIO Prefilled Syringe Carton - 40 mg/0.8 mL (2 count)
  IDACIO is supplied in a carton containing 2 alcohol preps and one tray. The tray contains two single-dose, 1 mL prefilled glass syringes with a 29 gauge staked ½ inch needle, each syringe providing 40 mg/0.8 mL of IDACIO. The syringe plunger stopper and needle cover are not made with natural rubber latex.
  The NDC number is 65219-556-18.
- IDACIO Single-Dose Institutional Use Vial Kit - 40 mg/0.8 mL.
  IDACIO is supplied in a carton containing 1 sterile single-use syringe, 1 sterile needle, 1 vial adapter, 2 alcohol preps and 1 glass vial providing 40 mg/0.8 mL of IDACIO. The vial stopper is not made with natural rubber latex. The NDC number is 65219-558-08.

Storage and Stability

Do not use beyond the expiration date on the container. IDACIO must be refrigerated at 36°F to 46°F (2°C to 8°C). DO NOT FREEZE. Do not use if frozen even if it has been thawed.

Store in original carton until time of administration to protect from light.

If needed, for example when traveling, IDACIO may be stored at room temperature up to a maximum of 77°F (25°C) for a period of up to 28 days, with protection from light. IDACIO should be discarded if not used within the 28-day period. Record the date when IDACIO is first removed from the refrigerator in the spaces provided on the carton.

Do not store IDACIO in extreme heat or cold.

17 PATIENT COUNSELING INFORMATION

Advise the patient or caregiver to read the FDA-approved patient labeling (Medication Guide and Instructions for Use).

Infections

Inform patients that IDACIO may lower the ability of their immune system to fight infections. Instruct patients of the importance of contacting their doctor if they develop any symptoms of infection, including tuberculosis, invasive fungal infections, and reactivation of hepatitis B virus infections [see Warnings and Precautions (5.1, 5.2, 5.4)].

Malignancies

Counsel patients about the risk of malignancies while receiving IDACIO [see Warnings and Precautions (5.2)]

Hypersensitivity Reactions

Advise patients to seek immediate medical attention if they experience any symptoms of severe hypersensitivity reactions.

Other Medical Conditions

Advise patients to report any signs of new or worsening medical conditions such as congestive heart failure, neurological disease, autoimmune disorders, or cytopenias. Advise patients to report any symptoms suggestive of a cytopenia such as bruising, bleeding, or persistent fever [see Warnings and Precautions (5.5, 5.6, 5.8, 5.9)].

Instructions on Injection Technique

Inform patients that the first injection is to be performed under the supervision of a qualified health care professional. If a patient or caregiver is to administer IDACIO, instruct them in injection techniques and assess their ability to inject subcutaneously to ensure the proper administration of IDACIO [see Instructions for Use].

For patients who will use the IDACIO Pen, tell them to:

- Remove the needle cap of the Pen and push and hold the Pen firmly against the skin on the chosen injection site.
- Activate Pen by pressing the injection button. The click means the start of the injection.
- Keep holding the IDACIO Pen against their skin until the injection has finished.
- Will know that the injection has finished when the syringe plunger moves all the way down to the bottom of the transparent syringe housing to enable the safety guard to cover the needle

Instruct patients to dispose of their used needles and syringes or used Pen in a FDA-cleared sharps disposal container immediately after use. Instruct patients not to dispose of loose needles and syringes or Pens in their household trash. Instruct patients that if they do not have a FDA-cleared sharps disposal container, they may use a household container that is made of a heavy-duty plastic, can be closed with a tight-fitting and puncture-resistant lid without sharps being able to come out, upright and stable during use, leak-resistant, and properly labeled to warn of hazardous waste inside the container.

Instruct patients that when their sharps disposal container is almost full, they will need to follow their community guidelines for the correct way to dispose of their sharps disposal container. Instruct patients that there may be state or local laws regarding disposal of used needles and syringes. Refer patients to the FDA's website at http://www.fda.gov/safesharpsdisposal for more information about safe sharps disposal, and for specific information about sharps disposal in the state that they live in.

Instruct patients not to dispose of their used sharps disposal container in their household trash unless their community guidelines permit this. Instruct patients not to recycle their used sharps disposal container.

Manufactured by: Fresenius Kabi USA, LLC
Lake Zurich, IL 60047, U.S.A
US License Number 2146

MEDICATION GUIDE
IDACIO® (i-DAS-i-oh)
(adalimumab-aacf)
injection, for subcutaneous use

Read the Medication Guide that comes with IDACIO before you start taking it and each time you get a refill. There may be new information. This Medication Guide does not take the place of talking with your healthcare provider about your medical condition or treatment.

What is the most important information I should know about IDACIO?
IDACIO is a medicine that affects your immune system. IDACIO can lower the ability of your immune system to fight infections. Serious infections have happened in people taking adalimumab products. These serious infections include tuberculosis (TB) and infections caused by viruses, fungi or bacteria that have spread throughout the body. Some people have died from these infections.

- Your healthcare provider should test you for TB before starting IDACIO.
- Your healthcare provider should check you closely for signs and symptoms of TB during treatment with IDACIO.

You should not start taking IDACIO if you have any kind of infection unless your healthcare provider says it is okay.
Before starting IDACIO, tell your healthcare provider if you:

- think you have an infection or have symptoms of an infection such as:
  - fever, sweats, or chills
  - muscle aches
  - cough
  - shortness of breath
  - blood in phlegm
  - warm, red, or painful skin or sores on your body
  - diarrhea or stomach pain
  - burning when you urinate or urinate more often than normal
  - feel very tired
  - weight loss
- are being treated for an infection.
- get a lot of infections or have infections that keep coming back.
- have diabetes
- have TB or have been in close contact with someone with TB.
- were born in, lived in, or traveled to countries where there is more risk for getting TB. Ask your healthcare provider if you are not sure.
- live or have lived in certain parts of the country (such as the Ohio and Mississippi River valleys) where there is an increased risk for getting certain kinds of fungal infections (histoplasmosis, coccidioidomycosis, or blastomycosis). These infections may happen or become more severe if you use IDACIO. Ask your healthcare provider if you do not know if you have lived in an area where these infections are common.
- have or have had hepatitis B
- use the medicine ORENCIA (abatacept), KINERET (anakinra), RITUXAN (rituximab), IMURAN (azathioprine), or PURINETHOL (6–mercaptopurine, 6-MP).
- are scheduled to have major surgery.

After starting IDACIO, call your healthcare provider right away if you have an infection, or any sign of an infection.
IDACIO can make you more likely to get infections or make any infection that you may have worse.
Cancer

- For children and adults taking Tumor Necrosis Factor (TNF)-blockers, including IDACIO, the chances of getting cancer may increase.
- There have been cases of unusual cancers in children, teenagers, and young adults using TNF-blockers.
- People with rheumatoid arthritis (RA), especially more serious RA, may have a higher chance for getting a kind of cancer called lymphoma.
- If you use TNF blockers including IDACIO your chance of getting two types of skin cancer may increase (basal cell cancer and squamous cell cancer of the skin). These types of cancer are generally not life-threatening if treated. Tell your healthcare provider if you have a bump or open sore that does not heal.
- Some people receiving TNF blockers including IDACIO developed a rare type of cancer called hepatosplenic T-cell lymphoma. This type of cancer often results in death. Most of these people were male teenagers or young men. Also, most people were being treated for Crohn's disease or ulcerative colitis with another medicine called IMURAN (azathioprine) or PURINETHOL (6-mercaptopurine, 6–MP).

What is IDACIO?
IDACIO is a medicine called a Tumor Necrosis Factor (TNF) blocker. IDACIO is used:

- To reduce the signs and symptoms of:
  - moderate to severe RA in adults. IDACIO can be used alone, with methotrexate, or with certain other medicines.
  - moderate to severe polyarticular juvenile idiopathic arthritis (JIA) in children 2 years and older. IDACIO can be used alone, or with methotrexate.
  - psoriatic arthritis (PsA) in adults. IDACIO can be used alone or with certain other medicines.
  - ankylosing spondylitis (AS) in adults.
  - moderate to severe hidradenitis suppurativa (HS) in adults.
- To treat moderate to severe Crohn's disease (CD) in adults and children 6 years of age and older.
- To treat moderate to severe ulcerative colitis (UC) in adults. It is not known if adalimumab products are effective in people who stopped responding to or could not tolerate TNF-blocker medicines.
- To treat moderate to severe chronic (lasting a long time) plaque psoriasis (Ps) in adults who have the condition in many areas of their body and who may benefit from taking injections or pills (systemic therapy) or phototherapy (treatment using ultraviolet light alone or with pills).
- To treat non-infectious intermediate, posterior, and panuveitis in adults.

What should I tell my healthcare provider before taking IDACIO?
IDACIO may not be right for you. Before starting IDACIO, tell your healthcare provider about all of your medical conditions, including if you:

- have an infection. See “What is the most important information I should know about IDACIO?”
- have or have had cancer.
- have any numbness or tingling or have a disease that affects your nervous system such as multiple sclerosis or Guillain-Barré syndrome.
- have or had heart failure.
- have recently received or are scheduled to receive a vaccine. You may receive vaccines, except for live vaccines while using IDACIO. Children should be brought up to date with all vaccines before starting IDACIO.
- are allergic to IDACIO or to any of its ingredients. See the end of this Medication Guide for a list of ingredients in IDACIO.
- are pregnant or plan to become pregnant, breastfeeding or plan to breastfeed. You and your healthcare provider should decide if you should take IDACIO while you are pregnant or breastfeeding.
- have a baby and you were using IDACIO during your pregnancy. Tell your baby's healthcare provider before your baby receives any vaccines.

Tell your healthcare provider about all the medicines you take, including prescription and over-the-counter medicines, vitamins, and herbal supplements.
Especially tell your healthcare provider if you use:

- ORENCIA (abatacept), KINERET (anakinra), REMICADE (infliximab), ENBREL (etanercept), CIMZIA (certolizumab pegol) or SIMPONI (golimumab), because you should not use IDACIO while you are also using one of these medicines.
- RITUXAN (rituximab). Your healthcare provider may not want to give you IDACIO if you have received RITUXAN (rituximab) recently.
- IMURAN (azathioprine) or PURINETHOL (6–mercaptopurine, 6-MP).

Keep a list of your medicines with you to show your healthcare provider and pharmacist each time you get a new medicine.

How should I take IDACIO?

- IDACIO is given by an injection under the skin. Your healthcare provider will tell you how often to take an injection of IDACIO. This is based on your condition to be treated. Do not inject IDACIO more often than you were prescribed.
- See the Instructions for Use inside the carton for complete instructions for the right way to prepare and inject IDACIO.
- Make sure you have been shown how to inject IDACIO before you do it yourself. If you have any questions about giving yourself an injection, you can call your healthcare provider or the patient support program at 1-833-522-4227. Someone you know can also help you with your injection after they have been shown how to prepare and inject IDACIO.
- Do not try to inject IDACIO yourself until you have been shown the right way to give the injections. If your healthcare provider decides that you or a caregiver may be able to give your injections of IDACIO at home, you should receive training on the right way to prepare and inject IDACIO.
- Do not miss any doses of IDACIO unless your healthcare provider says it is okay. If you forget to take IDACIO, inject a dose as soon as you remember. Then, take your next dose at your regular scheduled time. This will put you back on schedule. In case you are not sure when to inject IDACIO, call your healthcare provider or pharmacist.
- If you take more IDACIO than you were told to take, call your healthcare provider.

What are the possible side effects of IDACIO?
IDACIO can cause serious side effects, including:
See “What is the most important information I should know about IDACIO?”

- Serious Infections.
  Your healthcare provider will examine you for TB and perform a test to see if you have TB. If your healthcare provider feels that you are at risk for TB, you may be treated with medicine for TB before you begin treatment with IDACIO and during treatment with IDACIO. Even if your TB test is negative your healthcare provider should carefully monitor you for TB infections while you are taking IDACIO. People who had a negative TB skin test before receiving adalimumab products have developed active TB. Tell your healthcare provider if you have any of the following symptoms while taking or after taking IDACIO:
  - cough that does not go away
  - weight loss
  - low grade fever
  - loss of body fat and muscle (wasting)
- Hepatitis B infection in people who carry the virus in their blood.
  If you are a carrier of the hepatitis B virus (a virus that affects the liver), the virus can become active while you use IDACIO. Your healthcare provider should do blood tests before you start treatment, while you are using IDACIO, and for several months after you stop treatment with IDACIO. Tell your healthcare provider if you have any of the following symptoms of a possible hepatitis B infection:
  - muscle aches
  - feel very tired
  - dark urine
  - skin or eyes look yellow
  - little or no appetite
  - vomiting
  - clay-colored bowel movements
  - fever
  - chills
  - stomach discomfort
  - skin rash
- Allergic reactions. Allergic reactions can happen in people who use IDACIO. Call your healthcare provider or get medical help right away if you have any of these symptoms of a serious allergic reaction:
  - Hives
  - trouble breathing
  - swelling of your face, eyes, lips or mouth
- Nervous system problems. Signs and symptoms of a nervous system problem include numbness or tingling, problems with your vision, weakness in your arms or legs, and dizziness.
- Blood problems. Your body may not make enough of the blood cells that help fight infections or help to stop bleeding. Symptoms include a fever that does not go away, bruising or bleeding very easily, or looking very pale.
- New heart failure or worsening of heart failure you already have. Call your healthcare provider right away if you get new worsening symptoms of heart failure while taking IDACIO, including:
  - shortness of breath
  - sudden weight gain
  - swelling of your ankles or feet
- Immune reactions including a lupus-like syndrome. Symptoms include chest discomfort or pain that does not go away, shortness of breath, joint pain, or a rash on your cheeks or arms that gets worse in the sun. Symptoms may improve when you stop IDACIO.
- Liver Problems. Liver problems can happen in people who use TNF-blocker medicines. These problems can lead to liver failure and death. Call your healthcare provider right away if you have any of these symptoms:
  - feel very tired
  - poor appetite or vomiting
  - skin or eyes look yellow
  - pain on the right side of your stomach (abdomen)
- Psoriasis. Some people using adalimumab products had new psoriasis or worsening of psoriasis they already had. Tell your healthcare provider if you develop red scaly patches or raised bumps that are filled with pus. Your healthcare provider may decide to stop your treatment with IDACIO.

Call your healthcare provider or get medical care right away if you develop any of the above symptoms. Your treatment with IDACIO may be stopped.
The most common side effects of IDACIO include:

- injection site reactions: redness, rash, swelling, itching, or bruising. These symptoms usually will go away within a few days. Call your healthcare provider right away if you have pain, redness or swelling around the injection site that does not go away within a few days or gets worse.
- upper respiratory infections (including sinus infections).
- headaches.
- rash.

These are not all the possible side effects with IDACIO. Tell your healthcare provider if you have any side effect that bothers you or that does not go away. Ask your healthcare provider or pharmacist for more information. Call your doctor for medical advice about side effects. You may report side effects to FDA at 1-800-FDA-1088.

How should I store IDACIO?

- Store IDACIO in the refrigerator at 36ºF to 46ºF (2ºC to 8ºC). Store IDACIO in the original carton until use to protect it from light.
- Do not freeze IDACIO. Do not use IDACIO if frozen, even if it has been thawed.
- Refrigerated IDACIO may be used until the expiration date printed on the IDACIO carton. Pen or prefilled syringe. Do not use IDACIO after the expiration date.
- If needed, for example when you are traveling, you may also store IDACIO at room temperature up to 77°F (25°C) for up to 28 days. Store IDACIO in the original carton until use, to protect it from light.
- Throw away IDACIO if it has been kept at room temperature and not been used within 28 days.
- Record the date you first remove IDACIO from the refrigerator in the spaces provided on the carton.
- Do not store IDACIO in extreme heat or cold.
- Do not use a Pen or prefilled syringe if the liquid is cloudy, discolored, or has flakes or particles in it.
- Do not drop or crush IDACIO. The prefilled syringe is glass.

Keep IDACIO, injection supplies, and all other medicines out of the reach of children.

General information about the safe and effective use of IDACIO.
Medicines are sometimes prescribed for purposes other than those listed in a Medication Guide. Do not use IDACIO for a condition for which it was not prescribed. Do not give IDACIO to other people, even if they have the same condition. It may harm them. This Medication Guide summarizes the most important information about IDACIO. If you would like more information, talk with your healthcare provider. You can ask your pharmacist or healthcare provider for information about IDACIO that is written for health professionals.

What are the ingredients in IDACIO?
Active ingredient: adalimumab-aacf
IDACIO 40 mg/0.8 mL Pen, IDACIO 40 mg/0.8 mL prefilled syringe and IDACIO 40 mg/0.8 mL institutional use vial kit.
Inactive ingredients: glacial acetic acid, trehalose, polysorbate 80, sodium chloride and Water for Injection. Sodium hydroxide is added as necessary to adjust pH.
Manufactured by: Fresenius Kabi USA, LLC, Lake Zurich, IL 60047, U.S.A.
For more product information go to www. IDACIO.com. You can enroll in a patient support program by calling 1-833-522-4227 or visiting the patient support program website: https://kabicare.us/.
U.S. License number 2146

This Medication Guide has been approved by the U.S. Food and Drug Administration

Approved: Jan/2024

INSTRUCTIONS FOR USE

Important information
Read the Medication Guide that comes with your IDACIO prefilled syringe for important information you need to know before using it.
Do not try to inject IDACIO yourself until you have been shown the right way to give the injections and have read and understand this Instructions for Use. If your doctor decides that you or a caregiver may be able to give your injections of IDACIO at home, you should receive training on the right way to prepare and inject IDACIO. It is important that you read, understand, and follow these instructions so that you inject IDACIO the right way. It is also important to talk to your doctor to be sure you understand your IDACIO dosing instructions. To help you remember when to inject IDACIO, you can mark your calendar ahead of time. Call your healthcare provider if you or your caregiver have any questions about the right way to inject IDACIO.

How should I store IDACIO?

- Store IDACIO in the refrigerator between 36°F to 46°F (2°C to 8°C). Store IDACIO in the original carton until use to protect it from light.
- Do not freeze IDACIO. Do not use IDACIO if frozen, even if it has been thawed.
- Refrigerated IDACIO may be used until the expiration date printed on the IDACIO carton, or prefilled syringe. Do not use IDACIO after the expiration date.
- If needed, for example when traveling, you may also store IDACIO at room temperature up to 77°F (25°C) for up to 28 days. Store IDACIO in the original carton until use to protect it from light.
- Throw away IDACIO if it has been kept at room temperature and not been used within 28 days.
- Record the date you first remove IDACIO from the refrigerator in the spaces provided on the carton.
- Do not store IDACIO in extreme heat or cold.
- Do not use a prefilled syringe if the liquid is cloudy, discolored, or has flakes or particles in it.
- Do not drop or crush IDACIO. The prefilled syringe is glass.
- Keep IDACIO, injection supplies, and all other medicines out of the reach of children.

How should I use IDACIO?

- Only use IDACIO prefilled syringe if your healthcare provider has instructed you on how to use it.
- Do not try to reuse the IDACIO prefilled syringe.
- Before injecting, let IDACIO sit at room temperature for 15-30 minutes after removing it from the refrigerator.
- Do not use an IDACIO prefilled syringe to give IDACIO to a child who weighs less than 66 pounds (30 kg).

1.1 Gather the supplies for your injection.

- You will need the following supplies for each injection of IDACIO (Figure D). Find a clean, flat surface to place the supplies on.
  - 1 alcohol prep
  - 1 cotton ball or gauze pad (not included in your IDACIO carton)
  - 1 IDACIO prefilled syringe (See Figures A and B)
  - Puncture-resistant sharps disposal container for IDACIO prefilled syringe disposal (not included in your IDACIO carton). See Step 7 “Dispose of used prefilled syringes”.

If you do not have all the supplies you need to give yourself an injection, go to a pharmacy or call your pharmacist.

1.2 Remove the carton of IDACIO prefilled syringes from the refrigerator (Figure E).

1.3 Check the expiration date (EXP:) on the side of the carton (Figure E).

- Do not use if the expiration date has passed.

1.4 Take one IDACIO prefilled syringe out of the original carton:

- Place two fingers on the middle of the clear needle guard
- Pull the syringe straight up and out of the packaging (Figure F)
- Put the syringe on a clean flat surface.
- Do not pick up the syringe by the plunger or the needle cap. Doing this could damage the syringe or activate the clear needle guard.

1.5 Return the remaining syringe in its original carton to the refrigerator (Figure G).

- See “How should I store IDACIO?” for information on how to store your unused syringe.

1.6 Take your IDACIO prefilled syringe out of the refrigerator 15-30 minutes before injecting to allow the liquid to reach room temperature (Figure H).

- Do not remove the needle cap while allowing it to reach room temperature.
- Do not warm the syringe in any other way (for example, do not warm it in a microwave or in hot water).

2.1 Make sure that:

- the name IDACIO appears on the prefilled syringe label (Figure I).
- the syringe, the clear needle guard, and the needle cap are not cracked or damaged (Figure K).
- the needle cap is securely attached (Figure L).
- the needle guard spring is not extended (Figure M).

2.2 Do not use and do call your doctor or pharmacist if:

- the IDACIO labeling has an expired date. Check the expiration date (EXP:) on the prefilled syringe label and do not use if the date has passed (Figure I).
- the prefilled syringe has been frozen or left in direct sunlight.
- IDACIO has been kept at room temperature for longer than 28 days or IDACIO has been stored above 77°F (25°C).
- the liquid in the prefilled syringe is cloudy, discolored or has flakes or particles in it. Make sure the liquid is clear and colorless to pale yellow. (Figure J).

See “How should I store IDACIO?” section at the beginning of this Instructions for Use.

3.1 Wash and dry your hands well (Figure N).

4.1 Choose an injection site on (Figure O):

- your lower abdomen (belly). If you choose your abdomen, do not use the area 2 inches around your belly button (navel) or
- the front of your thighs
- Choose a different site each time to reduce redness, irritation or other skin problems. Each new injection should be given at least 1 inch from a site you used before.
- Do not inject into skin that is:
  - sore (tender)
  - bruised
  - red
  - hard
  - scarred or where you have stretch marks.
- If you have psoriasis, do not inject directly into any raised, thick, red or scaly skin patches or lesions on your skin.
- Do not inject through your clothes.

5.1 Wipe the injection site with an alcohol prep using a circular motion (Figure P).

- Do not touch this area again before giving the injection.

5.2 Allow the skin to dry before injecting.

- Do not fan or blow on the clean area.

6.1 Remove the needle cap:

- Hold the syringe in one hand. With the other hand gently remove the needle cap (Figure Q).
- Throw away the needle cap.
- Do not touch the needle with your fingers or let the needle touch anything.

6.2 Position the syringe

- Hold the body of the prefilled syringe in one hand between the thumb and index finger. Hold the syringe in your hand like a pencil (Figure R).
- Do not pull back on the plunger at any time.
- With your other hand, gently squeeze the area of the cleaned skin and hold it firmly (Figure S).

6.3 Insert the needle

- Using a quick dart-like motion, insert the needle into the squeezed skin at a 45-degree angle (Figure T).

6.4 Inject IDACIO

- Slowly push the plunger all the way in until all the liquid is injected, and the syringe is empty (Figure T).
- The plunger must be pushed all the way down to be sure the full dose has been injected and the safety system is activated (Figure U).
- Do not remove the needle from the skin when the plunger is pushed all the way down.

6.5 Finish Injection

- Slowly remove your thumb upwards off of the plunger.
  This will allow the needle to move up into the clear needle guard and cover the entire needle (Figure V).
- Release the squeezed skin.
- Call your healthcare provider or pharmacist right away if:
  - you did not inject the full dose or
  - the clear needle guard does not activate after injecting.
- Do not reuse a syringe even if all of the medicine was not injected.
- Do not try to recap the needle as it could lead to a needle stick injury.
- Press a cotton ball or gauze pad over the injection site and hold it for 10 seconds (Figure W). Do not rub the injection site. You may have slight bleeding. This is normal.

7.1 Put your used prefilled syringes in a FDA-cleared sharps disposal container right away after use (Figure X). Do not throw away (dispose of) prefilled syringes in your household trash.

- If you do not have a FDA-cleared sharps disposal container, you may use a household container that is:
  - made of a heavy-duty plastic,
  - can be closed with a tight-fitting, puncture-resistant lid, without sharps being able to come out,
  - upright and stable during use,
  - leak resistant, and
  - properly labeled to warn of hazardous waste inside the container.
- When your sharps disposal container is almost full, you will need to follow your community guidelines for the right way to dispose of your sharps disposal container. There may be state or local laws about how you should throw away used needles and syringes. For more information about safe sharps disposal, and for specific information about sharps disposal in the state that you live in, go to the FDA's website at: http://www.fda.gov/safesharpsdisposal
- For the safety and health of you and others, used syringes must never be re-used.
- The used alcohol prep, cotton balls, dose trays and packaging may be placed in your household trash.
- Do not dispose of your used sharps disposal container in your household trash unless your community guidelines permit this. Do not recycle your used sharps disposal container.
- Always keep the sharps container out of the reach of children.

8.1 To help you remember when and where on your body to give your next injection, keep a record of the dates and injection sites used for your injections (Figure Y).

Manufactured by:
Fresenius Kabi USA, LLC
Lake Zurich, Illinois 60047
U.S. License No. 2146

This Instruction for Use has been approved by the U.S. Food and Drug Administration Approved : 12/2022

INSTRUCTIONS FOR USE

Read this Instructions for Use before using your IDACIO prefilled pen.

Do not try to inject IDACIO yourself until you have been shown the right way to give the injections and have read and understand this Instructions for Use. If your healthcare provider decides that you or a caregiver may be able to give your injections of IDACIO at home, you should receive training on the right way to prepare and inject IDACIO. It is important that you read, understand, and follow these instructions so that you inject IDACIO the right way. It is also important to talk to your healthcare provider to be sure you understand your IDACIO dosing instructions. To help you remember when to inject IDACIO, you can mark your calendar ahead of time. Call your healthcare provider if you or your caregiver have any questions about the right way to inject IDACIO.

Important information

- Read the Medication Guide that comes with your IDACIO prefilled pen for important information you need to know before using it.
- Call your healthcare provider if you have any questions about IDACIO or how to give your injection.
- IDACIO prefilled pen is for single-dose (one-time) use only.
- Do not share your IDACIO prefilled pen with another person.
  You may give another person an infection or get an infection from them.

Storing IDACIO prefilled pens

- Store IDACIO prefilled pen in the original carton to protect it from light.
- Store IDACIO prefilled pen in the refrigerator between 36°F to 46°F (2°C to 8°C).
- Do not freeze IDACIO. Do not use IDACIO if frozen, even if it has been thawed.
- Refrigerated IDACIO may be used until the expiration date printed on the IDACIO carton, dose tray or pen. Do not use IDACIO after the expiration date.
- If needed, for example when traveling, IDACIO prefilled pen can be stored at room temperature between 68°F to 77°F (20°C to 25°C) for up to 28 days.
- Throw away IDACIO if it has been kept at room temperature and not been used within 28 days.
- Record the date you first remove IDACIO from the refrigerator in the spaces provided on the carton.
- Throw away (dispose of) the IDACIO prefilled pen in a sharps disposal container if it has been stored above 77°F (25°C). (See Step 7 “Dispose of your prefilled pens”).
- Do not store IDACIO in extreme heat or cold.
- Do not use IDACIO if the liquid is cloudy, discolored, or has flakes or particles in it.
- Do not drop or crush IDACIO.
- Keep the IDACIO prefilled pen, injection supplies, and all other medicines out of the reach and sight of children.

Using the IDACIO prefilled pen

- Only use IDACIO prefilled pen if your healthcare provider has instructed you on how to use it.
- Do not try to reuse the IDACIO prefilled pen.
- Before injecting, let IDACIO sit at room temperature for 15-30 minutes after removing it from the refrigerator.
- Always inject IDACIO using the technique your healthcare provider taught you.
- Do not use an IDACIO prefilled pen to give IDACIO to a child who weighs less than 66 pounds (30 kg).
- Do not insert your fingers into the opening of the safety guard.
- Do not use the prefilled pen if the new carton is open or damaged.
- Do not use an IDACIO prefilled pen that has been frozen or left in direct sunlight.
- Do not use and do call your healthcare provider or pharmacist if: you drop or crush your IDACIO prefilled pen.

1.1 Gather the supplies for your injection.

- You will need the following supplies for each injection of IDACIO (figure C). Find a clean flat surface, such as a table or countertop, in a well-lit area.
  - 1 Alcohol prep
  - 1 cotton ball or gauze (not included in your IDACIO carton)
  - 1 IDACIO prefilled pen (see figure A)
  - Pucture-resistant sharps disposal container for IDACIO prefilled pen disposal (not included in your IDACIO carton. (See Step 7 “Dispose of used prefilled pens”).

If you do not have all the supplies you need to give yourself an injection, go to a pharmacy or call your pharmacist.

1.2 Remove the carton of IDACIO prefilled pens from the refrigerator (Figure D).

1.3 Check the expiration date (EXP:) on the side of the carton (Figure E).

Do not use if the expiration date has passed.

1.4 Take one IDACIO prefilled pen out of the original carton:

- Place two fingers on the label
- Pull the pen straight up and out of the packaging (Figure F)
- Place the capped pen on a clean flat surface

1.5 Return the remaining pen in its original carton to the refrigerator

(Figure G).

See “Storing IDACIO prefilled pens” for information on how to store your unused pen.

1.6 Let the IDACIO prefilled pen sit at room temperature for 15-30 minutes before use to allow the medicine to reach room temperature (Figure H).

- Do not warm the pen in any other way, such as in a microwave, hot water, or direct sunlight.
- Do not remove the needle cap until you are ready to inject.

2.1 Wash your hands well with soap and water and dry them with a clean towel (Figure I).

3.1 Check the transparent syringe housing to make sure that:

- the liquid is clear and colorless to pale yellow, and
  free of particles and flakes (Figure J).
- the syringe is not cracked or damaged.
  (Figure J).

Do not use the prefilled pen if the liquid is cloudy or colored, if the liquid has particles or flakes in it, or if the prefilled pen looks damaged. Dispose of the pen in your sharps disposal container (see Step 7 “Dispose of your prefilled pens”) and call your healthcare provider or pharmacist.

3.2 Check the prefilled pen label to make sure that:

- the name on the pen says IDACIO
  (Figure K).
- the expiration date (EXP:) on the pen
  has not passed (Figure K).

Do not use the prefilled pen if the label does not have IDACIO on it or the expiration date has passed. Dispose of the pen in your sharps disposal container (see Step 7 “Dispose of used prefilled pens”) and call your healthcare provider or pharmacist.

4.1 Choose an injection site on

- your stomach (abdomen). If you choose your stomach, do not use the area 2 inches around your belly button (navel) or
- the front of your thighs (Figure L)

Only inject into injection sites shown (Figure L).

4.2 Choose a different site (at least one inch away from your last injection site) for each injection to reduce redness, irritation or other skin problems. Each new injection should be given at least 1 inch from a site you used before.

- Do not inject IDACIO into skin that is sore (tender), bruised, red, hard, scarred or where you have stretch marks or tattoos.
- If you have psoriasis, do not inject into any lesions or red, thick, raised or scaly patches.
- Do not inject through your clothes.

5.1 Wipe the skin of your injection site with an alcohol swab using a circular motion to clean it (Figure M).

Let the skin dry before injecting.

Do not blow on or touch the injection site again after cleaning.

6.1 Remove the needle cap

- Hold the pen upwards.
- Remove the needle cap with your other hand by pulling the cap straight off (Figure N).

Do not twist the cap.

Do not insert your fingers into the opening of the safety guard

You may see a few drops of liquid at the needle tip. This is normal

- Dispose of the needle cap in your sharps disposal container.

6.2 Position the pen

- Hold the pen so that you can see the transparent syringe housing.
- Place your thumb above (not touching) the yellow injection button (Figure O)
- Place the pen straight and flat against your skin at a 90° angle (Figure P).

6.3 Administer the Injection

- Push and hold the pen firmly against your skin until the safety guard is fully pushed down. This will unlock the injection button (Figure Q).
- Push the injection button with your thumb (Figure R). You will hear a loud ‘click', which means the injection has started.
- Continue to hold the pen firmly.
- Watch the syringe plunger to make sure it moves all the way down to the bottom of the transparent syringe housing (Figure R).
- Continue holding the pen for 5 seconds
  after the syringe plunger has reached the bottom of the transparent syringe housing. (Figure S)

Do not lift the pen from the skin until the syringe plunger has moved all the way down and you have waited 5 seconds.

- Lift the pen from your skin (Figure T).
  The safety guard will slide down and lock into place to cover the needle (Figure T).

Do not recap the pen.

Call your healthcare provider or pharmacist if you have any problem with your injection.

6.4 If there is blood or liquid on the injection site, gently press a cotton ball or gauze on the skin (Figure U).

Do not rub the injection site

You may use an adhesive bandage if needed.

7.1 Put your used prefilled pens in a FDA-cleared sharps disposal container right away after use (Figure V).

Do not throw away (dispose of) prefilled pens in your household trash.

- If you do not have a FDA-cleared sharps disposal container, you may use a household container that is:
  - made of a heavy-duty plastic,
  - can be closed with a tight-fitting, puncture-resistant lid, without sharps being able to come out,
  - upright and stable during use,
  - leak-resistant, and
  - properly labeled to warn of hazardous waste inside the container.
- When your sharps disposal container is almost full, you will need to follow your community guidelines for the right way to dispose of your sharps disposal container. There may be state or local laws about how you should dispose of used needles and pens.
- For more information about safe sharps disposal, and for specific information about sharps disposal in the state that you live in, go to the FDA's website at: http://www.fda.gov/safesharpsdisposal

Do not dispose of your used sharps disposal container in your household trash unless your community guidelines permit this.

Do not recycle your used sharps disposal container.

Always keep the sharps container out of the reach of children.

8.1 To help you remember when and where on your body to give your next injection, keep a record of the dates and injection sites used for your injections (Figure W).

Manufactured by:
Fresenius Kabi USA, LLXC
Lake Zurich, Illinois 60047
U.S. License No. 2146

This Instructions for Use has been approved by the U. S. Food and Drug Administration Approved: 12/2022

Read this Instructions for Use before using your IDACIO prefilled pen.

Do not try to inject IDACIO yourself until you have been shown the right way to give the injections and have read and understand this Instructions for Use. If your healthcare provider decides that you or a caregiver may be able to give your injections of IDACIO at home, you should receive training on the right way to prepare and inject IDACIO. It is important that you read, understand, and follow these instructions so that you inject IDACIO the right way. It is also important to talk to your healthcare provider to be sure you understand your IDACIO dosing instructions. To help you remember when to inject IDACIO, you can mark your calendar ahead of time. Call your healthcare provider if you or your caregiver have any questions about the right way to inject IDACIO.

Important information

- Read the Medication Guide that comes with your IDACIO prefilled pen for important information you need to know before using it.
- Call your healthcare provider if you have any questions about IDACIO or how to give your injection.
- Each IDACIO prefilled pen is for single-dose (one-time) use only.
- Do not share your IDACIO prefilled pen with another person.
  You may give another person an infection or get an infection from them.

Storing IDACIO prefilled pens

- Store IDACIO prefilled pen in the original carton to protect it from light.
- Store IDACIO prefilled pen in the refrigerator between 36°F to 46°F (2°C to 8°C).
- Do not freeze IDACIO. Do not use IDACIO if frozen, even if it has been thawed.
- Refrigerated IDACIO may be used until the expiration date printed on the IDACIO carton, dose tray or pen. Do not use IDACIO after the expiration date.
- If needed, for example when traveling, IDACIO prefilled pen can be stored at room temperature between 68°F to 77°F (20°C to 25°C) for up to 28 days.
- Throw away the IDACIO prefilled pens if it has been kept at room temperature and not been used within 28 days.
- Record the date you first removed the IDACIO prefilled pens from the refrigerator in spaces provided on the carton.
- Throw away (dispose of) the IDACIO prefilled pen in a sharps disposal container if it has been stored above 77°F (25°C). (See Step 7 “Dispose of your prefilled pens”).
- Do not store IDACIO in extreme heat or cold.
- Do not use IDACIO if the liquid is cloudy, discolored, or has flakes or particles in it.
- Do not drop or crush IDACIO.
- Keep the IDACIO prefilled pen, injection supplies, and all other medicines out of the reach and sight of children.

Using the IDACIO prefilled pen

- Only use IDACIO prefilled pen if your healthcare provider has instructed you on how to use it.
- Do not try to reuse the IDACIO prefilled pen.
- Before injecting, let IDACIO sit at room temperature for 15-30 minutes after removing it from the refrigerator.
- Always inject IDACIO using the technique your healthcare provider taught you.
- Do not insert your fingers into the opening of the safety guard.
- Do not use the prefilled pen if the new carton is open or damaged.
- Do not use an IDACIO prefilled pen that has been frozen or left in direct sunlight.
- Do not use and do call your healthcare provider or pharmacist if you drop or crush your IDACIO prefilled pen.

1.1 Your Starter Package includes multiple alcohol preps and prefilled pens for your starter treatment period.

Always make sure to use a new alcohol prep whenever you use a new pen.

Gather the supplies for your injection.

- You will need the following supplies for each injection of IDACIO (figure C). Find a clean flat surface, such as a table or countertop, in a well-lit area.
  - 1 Alcohol swab
  - 1 cotton ball or gauze (not included in your IDACIO carton)
  - 1 IDACIO prefilled pen (see figure A)
  - Puncture-resistant sharps disposal container for IDACIO prefilled pen disposal (not included in your IDACIO carton. (See Step 7 “Dispose of used prefilled pens”).

If you do not have all the supplies you need to give yourself an injection, go to a pharmacy or call your pharmacist.

1.2 Remove the pack of IDACIO prefilled pens from the refrigerator (Figure D).

1.3 Check the expiration date (EXP:) on the side of the pack (Figure E).

Do not use if the expiration date has passed.

1.4 Take the IDACIO prefilled pens you need for the day out of the original pack (refer to the schedule on the inner flap of your Starter Package for the number of prefilled pens to inject):

- Place two fingers on the label
- Pull the pen straight up and out of the packaging (Figure F)
- Place the capped pen on a clean flat surface

1.5 Return the remaining pen(s) in the original pack to the refrigerator (Figure G).

See “Storing IDACIO prefilled pens” for information on how to store your unused prefilled pen(s).

1.6 Let the IDACIO prefilled pen(s) sit at room temperature for 15-30 minutes before use to allow the medicine to reach room temperature (Figure H).

Do not warm the pen(s) in any other way, such as in a microwave, hot water, or direct sunlight.

Do not remove the needle cap until you are ready to inject.

2.1 Wash your hands well with soap and water and dry them with a clean towel (Figure I).

3.1 Check the transparent syringe housing to make sure that:

- the liquid is clear and colorless to pale yellow, and free of particles and flakes (Figure J).
- the syringe is not cracked or damaged. (Figure J).

Do not use the prefilled pen if the liquid is cloudy or colored, if the liquid has particles or flakes in it, or if the prefilled pen looks damaged. Dispose of the pen in your sharps disposal container (see Step 7 “Dispose of your prefilled pens”) and call your healthcare provider or pharmacist.

3.2 Check the prefilled pen label to make sure that:

- the name on the pen says IDACIO (Figure K).
- the expiration date (EXP:) on the pen has not passed (Figure K).

Do not use the prefilled pen if the label does not have IDACIO on it or the expiration date has passed. Dispose of the pen in your sharps disposal container (see Step 7 “Dispose of used prefilled pens”) and call your healthcare provider or pharmacist.

4.1 Choose an injection site on:

- your stomach (abdomen). If you choose your stomach, do not use the area 2 inches around your belly button (navel) or
- the front of your thighs (Figure L)

Only inject into injection sites shown (Figure L)

4.2 Choose a different site (at least one inch away from your last injection site) for each injection to reduce redness, irritation or other skin problems. Each new injection should be given at least 1 inch from a site you used before.

- Do not inject IDACIO into skin that is sore (tender), bruised, red, hard, scarred or where you have stretch marks or tattoos.
- If you have psoriasis, do not inject into any lesions or red, thick, raised or scaly patches.
- Do not inject through your clothes.

5.1 Using a new alcohol prep, clean the skin of your injection site using a circular motion (Figure M). Always make sure to use a new alcohol prep whenever you use a new pen.

Let the skin dry before injecting.

Do not blow on or touch the injection site again after cleaning.

6.1 Remove the needle cap

- Hold the pen upwards.
- Remove the needle cap with your other hand by pulling the cap straight off (Figure N).

Do not twist the cap.

Do not insert your fingers into the opening of the safety guard

You may see a few drops of liquid at the needle tip. This is normal

- Dispose of the needle cap in your sharps disposal container.

6.2 Position the pen

- Hold the pen so that you can see the transparent syringe housing.
- Place your thumb above (not touching) the yellow injection button (Figure O).
- Place the pen straight and flat against your skin at a 90° angle (Figure P).

6.3 Administer the Injection

- Push and hold the pen firmly against your skin until the safety guard is fully pushed down. This will unlock the injection button (Figure Q).
- Push the injection button (Figure R). You will hear a loud ‘click', which means the injection has started.
- Continue to hold the pen firmly.
- Watch the syringe plunger to make sure it moves all the way down to the bottom of the transparent syringe housing (Figure R).
- Continue holding the pen for 5 seconds
  after the syringe plunger has reached the bottom of the transparent syringe housing (Figure S).

Do not lift the pen from the skin until the syringe plunger has moved all the way down and you have waited 5 seconds.

- Lift the pen from your skin (Figure T). The safety guard will slide down and lock into place to cover the needle (Figure T).

Do not recap the pen.

Call your healthcare provider or pharmacist if you have any problem with your injection.

6.4 If there is blood or liquid on the injection site, gently press a cotton ball or gauze on the skin (Figure U).

Do not rub the injection site

You may use an adhesive bandage if needed.

6.5 Check the schedule on your Starter Package to know the number of prefilled pens needed for the day, and repeat the previous steps (step 3, step 4, step 5 and step 6) as needed.

7.1 Put your used prefilled pens in a FDA-cleared sharps disposal container right away after use (Figure V).

Do not throw away (dispose of) prefilled pens in your household trash.

- If you do not have a FDA-cleared sharps disposal container, you may use a household container that is:
  - made of a heavy-duty plastic,
  - can be closed with a tight-fitting, puncture-resistant lid,
    without sharps being able to come out,
  - upright and stable during use,
  - leak-resistant, and
  - properly labeled to warn of hazardous waste inside the
    container.
- When your sharps disposal container is almost full, you will need to follow your community guidelines for the right way to dispose of your sharps disposal container. There may be state or local laws about how you should Dispose of used needles and pens.
- For more information about safe sharps disposal, and for specific information about sharps disposal in the state that you live in, go to the FDA's website at: http://www.fda.gov/safesharpsdisposal

Do not dispose of your used sharps disposal container in your household trash unless your community guidelines permit this.

Do not recycle your used sharps disposal container.

Always keep the sharps container out of the reach of children.

8.1 To help you remember when and where on your body to give your next injection(s), keep a record of the dates and injection sites used for your injections (Figure W).

Manufactured by:
Fresenius Kabi USA, LLC
Lake Zurich, Illinois 60047
U.S. License No. 2146

This Instructions for Use has been approved by the U. S. Food and Drug Administration Approved: 12/2022

PACKAGE LABEL

Principal Display Panel – 0.8.mL - 4 unit Starter Pack Carton Label

Idacio®
adalimumab-aacf
Injection

40 mg / 0.8 mL

STARTER
PACK

NDC 65219-554-28

Rx Only

For Plaque Psoriasis or Uveitis

4x

For subcutaneous use only

4 single-dose prefilled pens

29
Gauge
Needle

Carton contains:

4 Single-dose prefilled pens with 29 gauge

1/2 inch length staked needle

4 Alcohol preps

1 Prescribing Information

1 Medication Guide

1 Instructions For Use

ATTENTION PHARMACIST:

Each patient is required to receive the enclosed Medication Guide.

Needle cover for syringe is not made with natural rubber latex.

The entire carton is to be dispensed as a unit.

FRESENIUS
KABI

PACKAGE LABEL

Principal Display Panel – 0.8.mL - 6 unit Starter Pack Carton Label

Idacio®
adalimumab-aacf
Injection

40 mg / 0.8 mL

STARTER
PACK

NDC 65219-554-38

Rx Only

For Crohn's Disease, Ulcerative Colitis,
Hidradenitis Suppurativa

6x

For subcutaneous use only

6 single-dose prefilled pens

29
Gauge
Needle

Carton contains:

6 Single-dose prefilled pens with 29 gauge

1/2 inch length staked needle

6 Alcohol preps

1 Prescribing Information

1 Medication Guide

1 Instructions For Use

ATTENTION PHARMACIST:

Each patient is required to receive the enclosed Medication Guide.

Needle cover for syringe is not made with natural rubber latex.

The entire carton is to be dispensed as a unit.

FRESENIUS
KABI

PACKAGE LABEL

Principal Display Panel – 0.8.mL - 2 Single-dose prefilled pens Carton Label

Idacio®
adalimumab-aacf
Injection

40 mg / 0.8 mL

NDC 65219-554-08

Rx Only

29 Gauge Needle

For subcutaneous use only

2 single-dose prefilled pens

Carton contains:
2 Single-dose prefilled pens with 29 gauge 1/2 inch length staked needle
2 Alcohol preps
1 Prescribing Information
1 Medication Guide
1 Instructions for Use

FRESENIUS
KABI

ATTENTION PHARMACIST:

Each patient is required to receive the enclosed Medication Guide.

Needle cover for syringe is not made with natural rubber latex. The entire carton is to be dispensed as a unit.

PACKAGE LABEL

Principal Display Panel – 0.8.mL - 2 Single-dose prefilled pens Carton Label

Idacio®
adalimumab-aacf
Injection

40 mg / 0.8 mL

NDC 65219-556-18

Rx Only

29 Gauge Needle

For subcutaneous use only

2 single-dose prefilled syringes

Carton contains:
2 Single-dose prefilled syringes with 29 gauge 1/2 inch length staked needle
2 Alcohol preps
1 Prescribing Information
1 Medication Guide
1 Instruction For Use

FRESENIUS
KABI

ATTENTION PHARMACIST:

Each patient is required to receive the enclosed Medication Guide.

Needle cover for syringe is not made with natural rubber latex. The entire carton is to be dispensed as a unit.